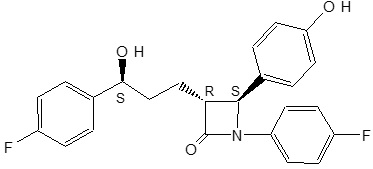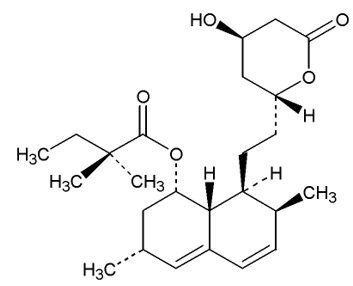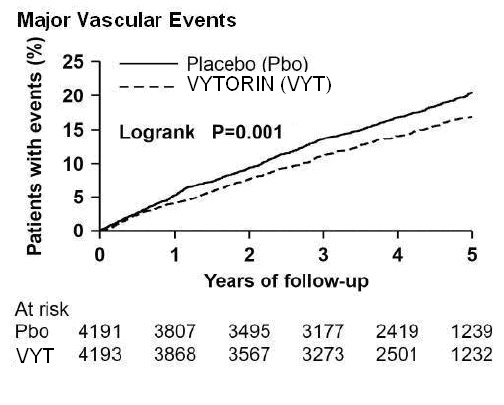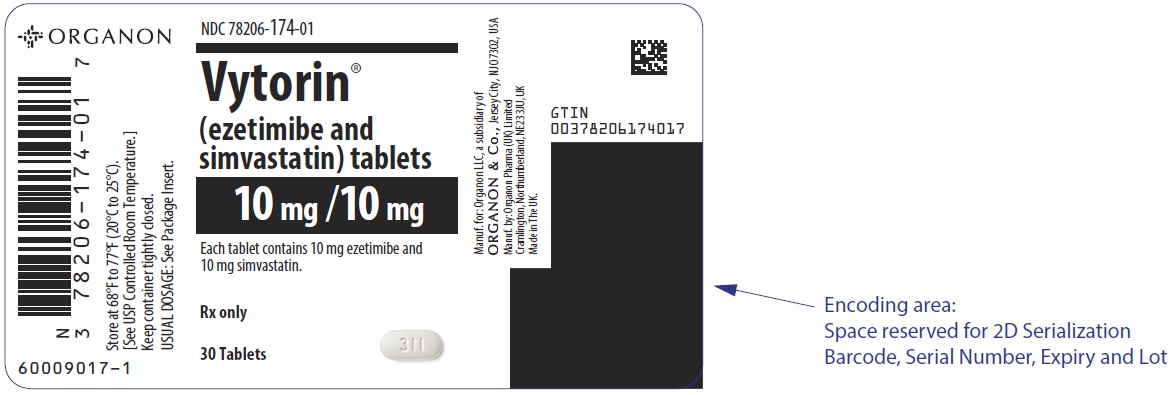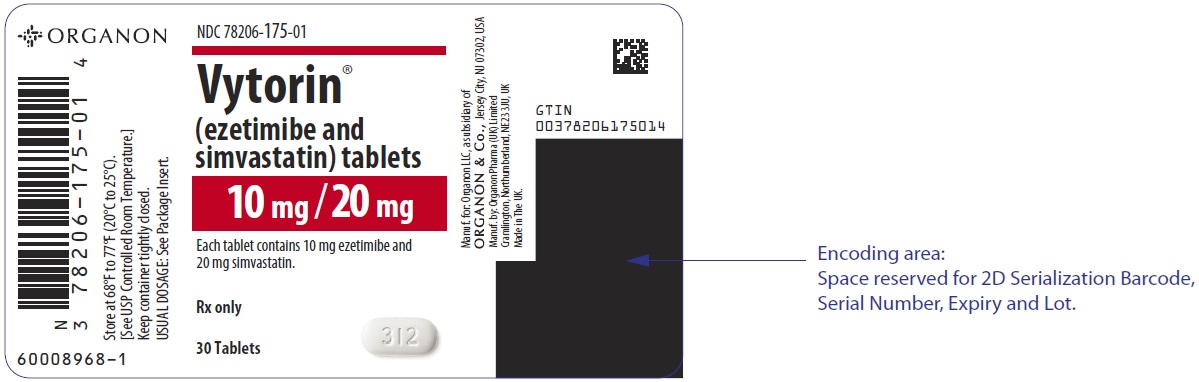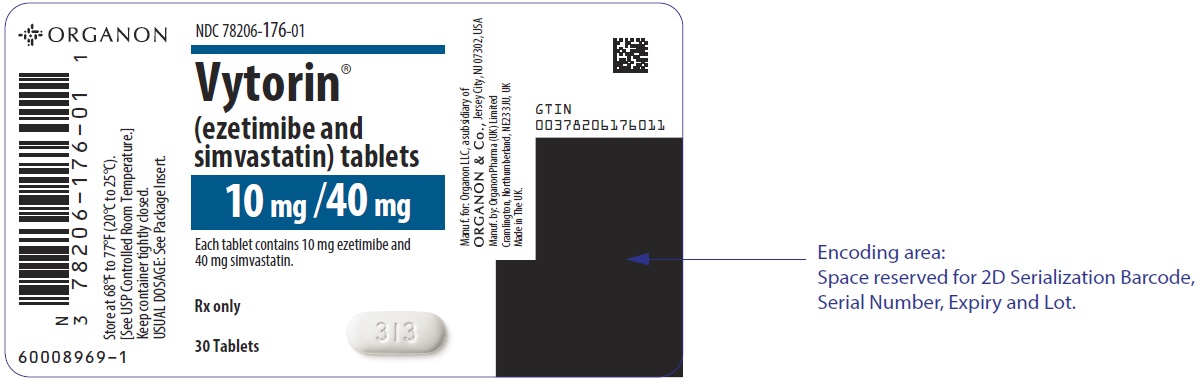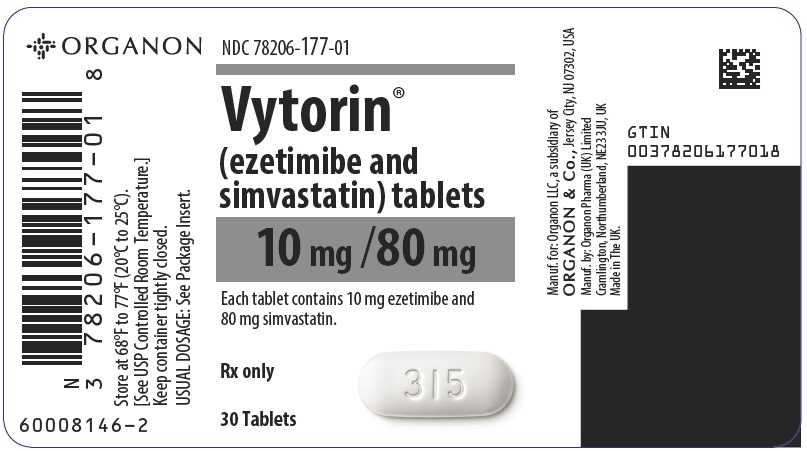 DRUG LABEL: VYTORIN
NDC: 78206-174 | Form: TABLET
Manufacturer: Organon LLC
Category: prescription | Type: HUMAN PRESCRIPTION DRUG LABEL
Date: 20260121

ACTIVE INGREDIENTS: EZETIMIBE 10 mg/1 1; SIMVASTATIN 10 mg/1 1
INACTIVE INGREDIENTS: BUTYLATED HYDROXYANISOLE; CITRIC ACID MONOHYDRATE; CROSCARMELLOSE SODIUM; HYPROMELLOSE, UNSPECIFIED; LACTOSE MONOHYDRATE; MAGNESIUM STEARATE; PROPYL GALLATE; MICROCRYSTALLINE CELLULOSE

HIGHLIGHTS OF PRESCRIBING INFORMATION

These highlights do not include all the information needed to use VYTORIN safely and effectively. See full prescribing information for VYTORIN.
VYTORIN® (ezetimibe and simvastatin) tablets, for oral use
Initial U.S. Approval: 2004

RECENT MAJOR CHANGES

Indications and Usage (1) | 2/2024
Dosage and Administration (2.1, 2.2, 2.3, 2.4, 2.5) | 2/2024
Contraindications, Pregnancy and Lactation (4) Removed | 2/2024
Warnings and Precautions (5.1, 5.2, 5.3) | 2/2024

1 INDICATIONS AND USAGE

VYTORIN is a combination of ezetimibe, a dietary cholesterol absorption inhibitor, and simvastatin, an HMG-CoA reductase inhibitor (statin) indicated: (1)

- As an adjunct to diet to reduce elevated low density lipoprotein cholesterol (LDL-C):
  - In adults with primary hyperlipidemia.
  - In adults and pediatric patients aged 10 years and older with heterozygous familial hypercholesterolemia (HeFH).
- As an adjunct to other LDL-C lowering therapies to reduce LDL-C in adults with homozygous familial hypercholesterolemia (HoFH).

Simvastatin
Simvastatin, when used as a component of VYTORIN, is indicated to reduce the risk of total mortality by reducing risk of coronary heart disease death, non-fatal myocardial infarction and stroke, and the need for coronary and non-coronary revascularization procedures in adults with established coronary heart disease, cerebrovascular disease, peripheral vascular disease, and/or diabetes, who are at high risk of coronary heart disease events.

2 DOSAGE AND ADMINISTRATION

- Important Dosage and Administration Information: (2.1)
  - Take VYTORIN orally once daily in the evening with or without food.
  - Maximum recommended dosage is VYTORIN 10/40 mg once daily. VYTORIN 10/80 mg daily dosage is restricted to patients who have been taking VYTORIN 10/80 mg daily chronically (e.g., for 12 months or more) without evidence of muscle toxicity.
  - For patients that require a high-intensity statin or are unable to achieve their LDL-C goal receiving VYTORIN 10/40 mg daily, prescribe alternative LDL-C-lowering treatment.
  - If as dose is missed, take the missed dose as soon as possible. Do not double the next dose.
  - Assess LDL-C when clinically appropriate, as early as 2 weeks after initiating VYTORIN, and adjust the dosage if necessary.
- Adults: Recommended dosage range of 10/10 mg to 10/40 mg once daily. (2.2)
- See full prescribing information for VYTORIN dosage modifications due to drug interactions. (2.3)
- Patients with Renal Impairment: Doses exceeding 10/20 mg should be used with caution and close monitoring in patients with moderate to severe renal impairment. (2.4)

3 DOSAGE FORMS AND STRENGTHS

Tablets (ezetimibe mg/simvastatin mg): 10/10, 10/20, 10/40, 10/80 (3)

4 CONTRAINDICATIONS

- Concomitant use of strong CYP3A4 inhibitors (select azole anti-fungals, macrolide antibiotics, anti-viral medications and nefazodone). (4)
- Concomitant use of cyclosporine, danazol or gemfibrozil. (4)
- Acute liver failure or decompensated cirrhosis. (4)
- Hypersensitivity to simvastatin, ezetimibe or any excipient of VYTORIN. (4)

5 WARNINGS AND PRECAUTIONS

- Myopathy and Rhabdomyolysis: Risk factors include age 65 years or greater, uncontrolled hypothyroidism, renal impairment, concomitant use with certain other drugs, and higher VYTORIN dosage. Chinese patients may be at higher risk for myopathy. Discontinue VYTORIN if markedly elevated CK levels occur or myopathy is diagnosed or suspected. Temporarily discontinue VYTORIN in patients experiencing an acute or serious condition at high risk of developing renal failure secondary to rhabdomyolysis. Inform patients of the risk of myopathy and rhabdomyolysis when starting or increasing VYTORIN dosage. Instruct patients to promptly report unexplained muscle pain, tenderness, or weakness, particularly if accompanied by malaise or fever. (5.1)
- Immune-Mediated Necrotizing Myopathy (IMNM): Rare reports of IMNM, an autoimmune myopathy, have been reported. Discontinue VYTORIN if IMNM is suspected. (5.2)
- Hepatic Dysfunction: Increases in serum transaminases have occurred, some persistent. Rare reports of fatal and non-fatal hepatic failure have occurred. Consider testing liver enzyme before initiating therapy and as clinically indicated thereafter. If serious hepatic injury with clinical symptoms and/or hyperbilirubinemia or jaundice occurs, promptly discontinue VYTORIN. (5.3)

6 ADVERSE REACTIONS

- Common (incidence ≥2% and greater than placebo) adverse reactions in clinical trials: headache, increased ALT, myalgia, upper respiratory tract infection, and diarrhea. (6.1)

To report SUSPECTED ADVERSE REACTIONS, contact Organon LLC, a subsidiary of Organon & Co., at 1-844-674-3200 or FDA at 1-800-FDA-1088 or www.fda.gov/medwatch.

7 DRUG INTERACTIONS

- See full prescribing information for details regarding concomitant use of VYTORIN with other drugs or grapefruit juice that increase the risk of myopathy and rhabdomyolysis. (2.3, 7.1)
- Cholestyramine: Combination decreases exposure of ezetimibe. (2.3, 7.2)
- Coumarin Anticoagulants: Obtain INR before VYTORIN initiation and monitor INR during VYTORIN dosage initiation or adjustment. (7.3)
- Digoxin: During VYTORIN initiation, monitor digoxin levels. (7.3)
- Fenofibrates: Combination increases exposure of ezetimibe. If cholelithiasis is suspected in a patient receiving ezetimibe and a fenofibrate, gallbladder studies are indicated and alternative lipid-lowering therapy should be considered. (7.3, 12.3)

8 USE IN SPECIFIC POPULATIONS

- Pregnancy: May cause fetal harm (8.1)
- Lactation: Breastfeeding not recommended during treatment with VYTORIN. (8.2)

FULL PRESCRIBING INFORMATION

1 INDICATIONS AND USAGE

VYTORIN

VYTORIN® is a combination of simvastatin and ezetimibe indicated:

- As an adjunct to diet to reduce elevated low density lipoprotein cholesterol (LDL-C):
  - In adults with primary hyperlipidemia.
  - In adults and pediatric patients aged 10 years and older with heterozygous familial hypercholesterolemia (HeFH).
- As an adjunct to other LDL-C-lowering therapies to reduce elevated LDL-C in adults with homozygous familial hypercholesterolemia (HoFH).

Simvastatin

Simvastatin, when used as a component of VYTORIN, is indicated to reduce the risk of total mortality by reducing risk of coronary heart disease death, non-fatal myocardial infarction and stroke, and the need for coronary and non-coronary revascularization procedures in adults with established coronary heart disease, cerebrovascular disease, peripheral vascular disease, and/or diabetes, who are at high risk of coronary heart disease events.

2 DOSAGE AND ADMINISTRATION

2.1 Important Dosage and Administration Information

- Take VYTORIN orally once daily in the evening with or without food.
- The maximum recommended dosage is VYTORIN 10/40 mg once daily. The VYTORIN 10/80 mg daily dosage is restricted to adult patients who have been taking VYTORIN 10/80 mg daily chronically (e.g., for 12 months or more) without evidence of muscle toxicity [see Warnings and Precautions (5.1)].
- For patients that require a high-intensity statin or are unable to achieve their LDL-C goal receiving VYTORIN 10/40 mg daily, prescribe alternative LDL-C-lowering treatment.
- If as dose is missed, take the missed dose as soon as possible. Do not double the next dose.
- Assess LDL-C when clinically appropriate, as early as 4 weeks after initiating VYTORIN, and adjust the dosage if necessary.

2.2 Recommended Dosage in Adult Patients

The recommended dosage range of VYTORIN 10/10 mg to 10/40 mg once a day.

2.3 Recommended Dosage in Pediatric Patients 10 Years of Age and Older with HeFH

The recommended dosage range of VYTORIN 10/10 mg to 10/40 mg once a day.

2.4 Recommended Dosage in Patients with Renal Impairment

Renal impairment is a risk factor for statin-associated myopathy. Doses of VYTORIN exceeding 10/20 mg should be used with caution and close monitoring in patients with moderate to severe renal impairment [see Warnings and Precautions (5.1) and Use in Specific Populations (8.6)].

There are no dosage adjustment recommendations for patients with mild renal impairment.

2.5 Dosage Modifications Due to Drug Interactions

Concomitant use of VYTORIN with the following drugs requires dosage modification of VYTORIN [see Warnings and Precautions (5.1) and Drug Interactions (7.1)].

Patients taking Lomitapide
Reduce the dosage of VYTORIN by 50%. Do not exceed VYTORIN 10/20 mg once daily (or 10/40 mg once daily for patients who have previously taken VYTORIN 10/80 mg daily chronically while taking lomitapide) [see Dosage and Administration (2.1)].

Patients taking Verapamil, Diltiazem, or Dronedarone
Do not exceed VYTORIN 10/10 mg once daily.

Patients taking Amiodarone, Amlodipine, or Ranolazine
Do not exceed VYTORIN 10/20 mg once daily.

Patients taking Bile Acid Sequestrants
In patients taking a bile acid sequestrant, administer VYTORIN at least 2 hours before or 4 hours after the bile acid sequestrant.

3 DOSAGE FORMS AND STRENGTHS

VYTORIN tablets:

- 10/10, (ezetimibe 10 mg and simvastatin 10 mg tablets) are white to off-white capsule-shaped and debossed with “311” on one side.
- 10/20, (ezetimibe 10 mg and simvastatin 20 mg tablets) are white to off-white capsule-shaped and debossed with “312” on one side.
- 10/40, (ezetimibe 10 mg and simvastatin 40 mg tablets) are white to off-white capsule-shaped and debossed with “313” on one side.
- 10/80, (ezetimibe 10 mg and simvastatin 80 mg tablets) are white to off-white capsule-shaped and debossed with “315” on one side.

4 CONTRAINDICATIONS

VYTORIN is contraindicated in the following conditions:

- Concomitant use of strong CYP3A4 inhibitors (select azole anti-fungals, macrolide antibiotics, anti-viral medications, and nefazodone) [see Drug Interactions (7.1)].
- Concomitant use of cyclosporine, danazol, or danazol [see Drug Interactions (7.1)].
- Acute liver failure or decompensated cirrhosis [see Warnings and Precautions (5.3)].
- Hypersensitivity to simvastatin, ezetimibe, or any excipients in VYTORIN. Hypersensitivity reactions, including anaphylaxis, angioedema, and Stevens-Johnson syndrome, have been reported [see Adverse Reactions (6.2)].

5 WARNINGS AND PRECAUTIONS

5.1 Myopathy and Rhabdomyolysis

VYTORIN may cause myopathy and rhabdomyolysis. Acute kidney injury secondary to myoglobinuria and rare fatalities have occurred as a result of rhabdomyolysis in patients treated with statins, including VYTORIN.

In clinical trials of 24,747 simvastatin-treated patients with a median follow-up of 4 years, the incidence of myopathy, defined as unexplained muscle weakness, pain, or tenderness accompanied by creatinine kinase (CK) increases greater than ten times the upper limit of normal (10 X ULN), were approximately 0.03%, 0.08%, and 0.61% in patients treated with simvastatin 20 mg, 40 mg, and 80 mg daily, respectively. In another clinical trial of 12,064 simvastatin-treated patients (with a history of myocardial infarction) with a mean follow-up of 6.7 years, the incidences of myopathy in patients taking simvastatin 20 mg and 80 mg daily were approximately 0.02% and 0.9%, respectively. The incidences of rhabdomyolysis (defined as myopathy with a CK >40 X ULN) in patients taking simvastatin 20 mg and 80 mg daily were approximately 0% and 0.4%, respectively [see Adverse Reactions (6.1)].

In the Trial of Heart and Renal Protection (SHARP), 9270 patients with chronic kidney disease were allocated to receive VYTORIN 10/20 mg daily (n=4650) or placebo (n=4620). During a median follow-up period of 4.9 years, the incidence of myopathy (defined as unexplained muscle weakness or pain with a serum creatine kinase [CK] >10 times upper limit of normal [ULN]) was 0.2% for VYTORIN and 0.1% for placebo: the incidence of rhabdomyolysis (defined as myopathy with a CK > 40 times ULN) was 0.09% for VYTORIN and 0.02% for placebo.

In postmarketing experience with ezetimibe, cases of myopathy and rhabdomyolysis have been reported. Most patients who developed rhabdomyolysis were taking a statin prior to initiating ezetimibe. However, rhabdomyolysis has been reported with ezetimibe monotherapy and with the addition of ezetimibe to agents known to be associated with increased risk of rhabdomyolysis, such as fibric acid derivatives. VYTORIN and a fenofibrate, if taking concomitantly, should both be immediately discontinued if myopathy is diagnosed or suspected.

Risk Factors for Myopathy

Risk factors for myopathy include age 65 years or greater, uncontrolled hypothyroidism, renal impairment, concomitant use with certain other drugs (including other lipid-lowering therapies), and higher VYTORIN dosage; Chinese patients on VYTORIN may be at higher risk for myopathy [see Contraindications (4), Drug Interactions (7.1), and Use in Specific Populations (8.8)]. The risk of myopathy is increased by elevated plasma levels of simvastatin and simvastatin acid. The risk is also greater in patients taking VYTORIN 80 mg daily compared with patients taking lower VYTORIN dosages and compared with patients using other statins with similar or greater LDL-C-lowering efficacy [see Adverse Reactions (6.1)].

Steps to Prevent or Reduce the Risk of Myopathy and Rhabdomyolysis

The concomitant use of strong CYP3A4 inhibitors with VYTORIN is contraindicated. If short-term treatment with strong CYP3A4 inhibitors is required, temporarily suspend VYTORIN during the duration of strong CYP3A4 inhibitor treatment. The concomitant use of VYTORIN with gemfibrozil, cyclosporine, or danazol is also contraindicated [see Contraindications (4) and Drug Interactions (7.1)].

VYTORIN dosage modifications are recommended for patients taking lomitapide, verapamil, diltiazem, dronedarone, amiodarone, amlodipine or ranolazine [see Dosage and Administration (2.5)]. VYTORIN use should be temporarily suspended in patients taking daptomycin. Lipid modifying doses (≥1 gram/day) of niacin, fibrates, colchicine, and grapefruit juice may also increase the risk of myopathy and rhabdomyolysis [see Drug Interactions (7.1)].

Use the 80 mg daily dosage of VYTORIN only in patients who have been taking simvastatin 80 mg daily chronically without evidence of muscle toxicity [see Dosage and Administration (2.1)]. If patients treated with VYTORIN 80 mg are prescribed an interacting drug that increases the risk for myopathy and rhabdomyolysis, switch to an alternate statin [see Drug Interactions (7.1)].

Discontinue VYTORIN if markedly elevated CK levels occur or if myopathy is either diagnosed or suspected. Muscle symptoms and CK increases may resolve if VYTORIN is discontinued. Temporarily discontinue VYTORIN in patients experiencing an acute or serious condition at high risk of developing renal failure secondary to rhabdomyolysis, e.g., sepsis; shock; severe hypovolemia; major surgery; trauma; severe metabolic, endocrine, or electrolyte disorders; or uncontrolled epilepsy.

Inform patients of the risk of myopathy and rhabdomyolysis when starting or increasing the VYTORIN dosage and advise patients receiving VYTORIN 80 mg of the increased risk of myopathy and rhabdomyolysis. Instruct patients to promptly report any unexplained muscle pain, tenderness or weakness, particularly if accompanied by malaise or fever.

5.2 Immune-Mediated Necrotizing Myopathy

There have been rare reports of immune-mediated necrotizing myopathy (IMNM), an autoimmune myopathy, associated with statin use, including reports of recurrence when the same or a different statin was administered. IMNM is characterized by proximal muscle weakness and elevated serum creatine kinase that persist despite discontinuation of statin treatment; positive anti-HMG CoA reductase antibody; muscle biopsy showing necrotizing myopathy without significant inflammation; and improvement with immunosuppressive agents. Additional neuromuscular and serologic testing may be necessary. Treatment with immunosuppressive agents may be required. Discontinue VYTORIN if IMNM is suspected.

5.3 Hepatic Dysfunction

Increases in serum transaminases have been reported with use of VYTORIN [see Adverse Reactions (6.1)]. In most cases, these changes appeared soon after initiation, were transient, were not accompanied by symptoms, and resolved or improved on continued therapy or after a brief interruption in therapy. Marked persistent increases of hepatic transaminases have also occurred with VYTORIN. There have been rare postmarketing reports of fatal and non-fatal hepatic failure in patients taking statins, including VYTORIN.

In three placebo-controlled, 12-week trials, the incidence of consecutive elevations (≥3 X ULN) in serum transaminases was 1.7% overall for patients treated with VYTORIN and appeared to be dose-related with an incidence of 2.6% for patients treated with VYTORIN 10/80. In controlled long-term (48-week) extensions, which included both newly-treated and previously-treated patients, the incidence of consecutive elevations (≥3 X ULN) in serum transaminases was 1.8% overall and 3.6% for patients treated with VYTORIN 10/80. These elevations in transaminases were generally asymptomatic, not associated with cholestasis, and returned to baseline after discontinuation of therapy or with continued treatment.

In SHARP, 9270 patients with chronic kidney disease were allocated to receive VYTORIN 10/20 mg daily (n=4650), or placebo (n=4620). During a median follow-up period of 4.9 years, the incidence of consecutive elevations of transaminases (>3 X ULN) was 0.7% for VYTORIN and 0.6% for placebo.

Patients who consume substantial quantities of alcohol and/or have a history of liver disease may be at increased risk for hepatic injury.

Consider liver enzyme testing before VYTORIN initiation and when clinically indicated thereafter. VYTORIN is contraindicated in patients with acute liver failure or decompensated cirrhosis [see Contraindications (4)]. If serious hepatic injury with clinical symptoms and/or hyperbilirubinemia or jaundice occurs, promptly discontinue VYTORIN.

5.4 Increases in HbA1c and Fasting Serum Glucose Levels

Increases in HbA1c and fasting serum glucose levels have been reported with statins, including VYTORIN. Optimize lifestyle measures, including regular exercise, maintaining a healthy body weight, and making healthy food choices.

6 ADVERSE REACTIONS

The following serious adverse reactions are discussed in greater detail in other sections of the label:

- Myopathy and Rhabdomyolysis [see Warnings and Precautions (5.1)]
- Immune-Mediated Necrotizing Myopathy [see Warnings and Precautions (5.2)]
- Hepatic Dysfunction [see Warnings and Precautions (5.3)]
- Increases in HbA1c and Fasting Serum Glucose Levels [see Warnings and Precautions (5.4)]

6.1 Clinical Trials Experience

Because clinical trials are conducted under widely varying conditions, adverse reaction rates observed in the clinical trials of a drug cannot be directly compared to rates in the clinical trials of another drug and may not reflect the rates observed in practice.

VYTORIN

In the VYTORIN (ezetimibe and simvastatin) placebo-controlled clinical trials database of 1420 patients (age range 20-83 years, 52% female, 87% White, 3% Black or African American, 3% Asians, 5% other races identified as Hispanic or Latino ethnicity) with a median treatment duration of 27 weeks, 5% of patients on VYTORIN and 2.2% of patients on placebo discontinued due to adverse reactions.

The most commonly reported adverse reactions (incidence ≥2% and greater than placebo) in controlled clinical trials were: headache (5.8%), increased ALT (3.7%), myalgia (3.6%), upper respiratory tract infection (3.6%), and diarrhea (2.8%). The most common adverse reactions in the group treated with VYTORIN that led to treatment discontinuation and occurred at a rate greater than placebo were: increased ALT (0.9%), myalgia (0.6%), increased AST (0.4%), and back pain (0.4%).

VYTORIN has been evaluated for safety in more than 10,189 patients in clinical trials.

Table 1 summarizes the frequency of clinical adverse reactions reported in ≥2% of patients treated with VYTORIN (n=1420) and at an incidence greater than placebo from four placebo-controlled trials.

Table 1 [Includes two placebo-controlled combination studies in which the active ingredients equivalent to VYTORIN were coadministered and two placebo-controlled studies in which VYTORIN was administered.] : Adverse Reactions Reported ≥2% of Patients Treated with VYTORIN at an Incidence Greater than Placebo Regardless of Causality
 | % Placebo N = 371 | % Ezetimibe 10 mg N = 302 | % Simvastatin [All doses.] N = 1234 | % VYTORIN N = 1420
Headache | 5.4 | 6.0 | 5.9 | 5.8
Upper respiratory tract infection | 2.7 | 5.0 | 5.0 | 3.6
Myalgia | 2.4 | 2.3 | 2.6 | 3.6
Diarrhea | 2.2 | 5.0 | 3.7 | 2.8
Pain in extremity | 1.3 | 3.0 | 2.0 | 2.3
Influenza | 0.8 | 1.0 | 1.9 | 2.3

Study of Heart and Renal Protection

In SHARP, 9270 patients were allocated to VYTORIN 10/20 mg daily (n=4650) or placebo (n=4620) for a median follow-up period of 4.9 years. The proportion of patients who permanently discontinued trial treatment as a result of either an adverse event or abnormal safety blood result was 10.4% vs. 9.8% among patients allocated to VYTORIN and placebo, respectively. Comparing those allocated to VYTORIN vs. placebo, the incidence of myopathy (defined as unexplained muscle weakness or pain with a serum CK >10 times ULN) was 0.2% vs. 0.1% and the incidence of rhabdomyolysis (defined as myopathy with a CK >40 times ULN) was 0.09% vs. 0.02%, respectively. Consecutive elevations of transaminases (>3 X ULN) occurred in 0.7% vs. 0.6%, respectively. Patients were asked about the occurrence of unexplained muscle pain or weakness at each trial visit: 21.5% vs. 20.9% patients ever reported muscle symptoms in the VYTORIN and placebo groups, respectively. Cancer was diagnosed during the trial in 9.4% vs. 9.5% of patients assigned to VYTORIN and placebo, respectively.

Ezetimibe

Other adverse reactions reported with ezetimibe in placebo-controlled studies, regardless of causality assessment: Musculoskeletal system disorders: arthralgia; Infections and infestations: sinusitis; Body as a whole – general disorders: fatigue.

Simvastatin

In a clinical outcome trial in which 12,064 adult patients with a history of myocardial infarction were treated with simvastatin (mean follow-up 6.7 years), the incidence of myopathy (defined as unexplained muscle weakness or pain with a serum creatine kinase [CK] >10 times (1200 U/L) upper limit of normal [ULN]) in patients taking simvastatin 20 mg and 80 mg daily was approximately 0.02% and 0.9% respectively. The incidence of rhabdomyolysis (defined as myopathy with a CK >40 times ULN) in patients taking simvastatin 20 mg and 80 mg daily was approximately 0% and 0.4%. The incidence of myopathy and rhabdomyolysis, was highest during the first year and then notably decreased during the subsequent years of treatment. In this trial, patients were carefully monitored and some interacting medicinal products were excluded.

Other adverse reactions reported with simvastatin in placebo-controlled clinical trials: atrial fibrillation; vertigo; abdominal pain, constipation, dyspepsia, flatulence, gastritis; eczema, rash; diabetes mellitus; bronchitis, sinusitis, urinary tract infections; asthenia, edema/swelling; and insomnia.

Laboratory Tests

Marked persistent increases of hepatic serum transaminases have been noted [see Warnings and Precautions (5.3)]. Elevated alkaline phosphatase and γ-glutamyl transpeptidase have been reported. About 5% of patients taking simvastatin had elevations of CK levels of 3 or more times the normal value on one or more occasions. This was attributable to the noncardiac fraction of CK [see Warnings and Precautions (5.1)].

6.2 Postmarketing Experience

The following adverse reactions have been identified during post-approval use of VYTORIN. Because these reactions are reported voluntarily from a population of uncertain size, it is not always possible to reliably estimate their frequency or establish a causal relationship to drug exposure.

Body as Whole: fever, chills, malaise, asthenia

Blood and Lymphatic System Disorders: anemia, thrombocytopenia, leukopenia, hemolytic anemia, positive ANA, ESR increase, eosinophilia

Gastrointestinal Disorders: pancreatitis, nausea, vomiting

Hepatobiliary Disorders: cholelithiasis, cholecystitis, elevations in liver transaminases including elevations more than 5 X ULN, hepatitis/jaundice, fatal and non-fatal hepatic failure

Immune System Disorders: hypersensitivity syndrome including: anaphylaxis, angioedema, lupus erythematous-like syndrome, dermatomyositis, vasculitis

Musculoskeletal and Connective Tissue Disorders: muscle cramps, immune-mediated necrotizing myopathy, rhabdomyolysis, myalgia, arthralgia, polymyalgia rheumatica, arthritis, elevated creatine phosphokinase

Nervous System Disorders: dizziness, depression, paresthesia, peripheral neuropathy, rare reports of cognitive impairment (e.g., memory loss, forgetfulness, amnesia, memory impairment, confusion) associated with statin use. Cognitive impairment was generally nonserious, and reversible upon statin discontinuation, with variable times to symptom onset (1 day to years) and symptom resolution (median of 3 weeks). There have been rare reports of new-onset or exacerbation of myasthenia gravis, including ocular myasthenia, and reports of recurrence when the same or a different statin was administered.

Skin and Subcutaneous Tissue Disorders: rash, pruritus, alopecia, a variety of skin changes (e.g., nodules, discoloration, dryness of skin/mucous membranes, changes to hair/nails), purpura, lichen planus, urticaria, photosensitivity, flushing, toxic epidermal necrolysis, erythema multiforme, including Stevens-Johnson syndrome.

Respiratory and Thoracic: interstitial lung disease, dyspnea

Reproductive System Disorders: erectile dysfunction

7 DRUG INTERACTIONS

VYTORIN

7.1 Drug Interactions that Increase the Risk of Myopathy and Rhabdomyolysis with VYTORIN

VYTORIN is a substrate of CYP3A4 and of the transport protein OATP1B1. VYTORIN plasma levels can be significantly increased with concomitant administration of inhibitors of CYP3A4 and OATP1B1.

Table 2 includes a list of drugs that increase the risk of myopathy and rhabdomyolysis when used concomitantly with VYTORIN and instructions for preventing or managing them [see Warnings and Precautions (5.1) and Clinical Pharmacology (12.3)].

Table 2: Drug Interactions that Increase the Risk of Myopathy and Rhabdomyolysis with VYTORIN
Strong CYP3A4 inhibitors
Clinical Impact: | Simvastatin is a substrate of CYP3A4. Concomitant use of strong CYP3A4 inhibitors with VYTORIN increases simvastatin exposure and increases the risk of myopathy and rhabdomyolysis, particularly with higher VYTORIN dosages.
Intervention: | Concomitant use of strong CYP3A4 inhibitors with VYTORIN is contraindicated [see Contraindications (4)]. If treatment with a CYP3A4 inhibitor is unavoidable, suspend VYTORIN during the course of strong CYP3A4 inhibitor treatment.
Examples: | Select azole anti-fungals (e.g., itraconazole, ketoconazole, posaconazole, and voriconazole), select macrolide antibiotics (e.g., erythromycin and clarithromycin, telithromycin), select HIV protease inhibitors (e.g., nelfinavir, ritonavir, and darunavir/ritonavir), select HCV protease inhibitors (e.g., boceprevir and telaprevir), cobicistat-containing products, and nefazodone.
Cyclosporine, Danazol, or Gemfibrozil
Clinical Impact: | The risk of myopathy and rhabdomyolysis is increased with concomitant use of cyclosporine, danazol, or gemfibrozil with VYTORIN. Gemfibrozil may cause myopathy when given alone.
Intervention: | Concomitant use of cyclosporine, danazol, or gemfibrozil with VYTORIN is contraindicated [see Contraindications (4)].
Amiodarone, Dronedarone, Ranolazine, or Calcium Channel Blockers
Clinical Impact: | The risk of myopathy and rhabdomyolysis is increased by concomitant use of amiodarone, dronedarone, ranolazine, or calcium channel blockers with VYTORIN.
Intervention: | For patients taking verapamil, diltiazem, or dronedarone, do not exceed VYTORIN 10/10 mg daily. For patients taking amiodarone, amlodipine, or ranolazine, do not exceed VYTORIN 10/20 mg daily [see Dosage and Administration (2.3)].
Lomitapide
Clinical Impact: | Simvastatin exposure is approximately doubled with concomitant use of lomitapide and the risk of myopathy and rhabdomyolysis is increased.
Intervention: | Reduce the dose of VYTORIN by 50% if initiating lomitapide. Do not exceed VYTORIN 10/20 mg daily (or VYTORIN 10/40 mg daily for patients who have previously taken VYTORIN 10/80 mg daily chronically) while taking lomitapide [see Dosage and Administration (2.1, 2.3)].
Daptomycin
Clinical Impact: | Cases of rhabdomyolysis have been reported with simvastatin administered with daptomycin. Both VYTORIN and daptomycin can cause myopathy and rhabdomyolysis when given alone and the risk of myopathy and rhabdomyolysis may be increased by coadministration.
Intervention: | If treatment with daptomycin is required, consider temporarily suspending VYTORIN during the course of daptomycin treatment.
Niacin
Clinical Impact: | Cases of myopathy and rhabdomyolysis have been observed with concomitant use of lipid modifying dosages of niacin-containing products (≥1 gram/day niacin) with VYTORIN. The risk of myopathy is greater in Chinese patients. In a clinical trial (median follow-up 3.9 years) of patients at high risk of CVD and with well-controlled LDL-C levels on simvastatin 40 mg/day with or without ezetimibe 10 mg/day, there was no incremental benefit on cardiovascular outcomes with the addition of lipid-modifying doses of niacin
Intervention: | Concomitant use of VYTORIN with lipid-modifying dosages of niacin is not recommended in Chinese patients [see Use in Specific Populations (8.8)]. For non-Chinese patients, consider if the benefit of using lipid-modifying doses of niacin concomitantly with VYTORIN outweighs the increased risk of myopathy and rhabdomyolysis. If concomitant use is decided, monitor patients for signs and symptoms of myopathy, particularly during initiation of therapy and during upward dose titration of either drug.
Fibrates (other than Gemfibrozil)
Clinical Impact: | Fibrates may cause myopathy when given alone. The risk of myopathy and rhabdomyolysis is increased with concomitant use of fibrates with VYTORIN.
Intervention: | Consider if the benefit of using fibrates concomitantly with VYTORIN outweighs the increased risk of myopathy and rhabdomyolysis. If concomitant use is decided, monitor patients for signs and symptoms of myopathy, particularly during initiation of therapy and during upward dose titration of either drug.
Colchicine
Clinical Impact: | Cases of myopathy and rhabdomyolysis have been reported with concomitant use of colchicine with VYTORIN.
Intervention: | Consider if the benefit of using colchicine concomitantly with VYTORIN outweighs the increased risk of myopathy and rhabdomyolysis. If concomitant use is decided, monitor patients for signs and symptoms of myopathy, particularly during initiation of therapy and during upward dose titration of either drug.
Grapefruit Juice
Clinical Impact: | Grapefruit juice can raise the plasma levels of simvastatin and may increase the risk of myopathy and rhabdomyolysis.
Intervention: | Avoid grapefruit juice when taking VYTORIN.

7.2 Drug Interactions that Decrease the Efficacy of VYTORIN

Table 3 presents drug interactions that may decrease the efficacy of VYTORIN and instructions for preventing or managing them.

Table 3: Drug Interactions that Decrease the Efficacy of VYTORIN
Bile Acid Sequestrants
Clinical Impact: | Concomitant cholestyramine administration decreased the mean exposure of total ezetimibe approximately 55%. The incremental LDL-C reduction due to adding VYTORIN to cholestyramine may be reduced by this interaction [see Clinical Pharmacology (12.3)].
Intervention: | In patients taking a bile acid sequestrant, administer VYTORIN at least 2 hours before or at least 4 hours after cholestyramine [see Dosage and Administration (2.3)].

7.3 VYTORIN’s Effect on Other Drugs

Table 4 presents VYTORIN’s effect on other drugs and instructions for preventing or managing them.

Table 4: VYTORIN Effects on Other Drugs
Coumarin Anticoagulants
Clinical Impact: | VYTORIN may potentiate the effect of coumarin anticoagulants and increase the INR. The concomitant use of simvastatin (20 to 40 mg) and coumarin anticoagulants increased the INR from a baseline of 1.7 to 1.8 in healthy subjects and from 2.6 to 3.4 in patients with hyperlipidemia. There are postmarketing reports of clinically evident bleeding and/or increased INR in patients taking concomitant statins (with or without ezetimibe) and coumarin anticoagulants.
Intervention: | In patients taking coumarin anticoagulants, obtain an INR before starting VYTORIN and frequently enough after initiation, dose titration, or discontinuation to ensure that no significant alteration in INR occurs. Once the INR is stable, monitor INR at regularly recommended intervals.
Digoxin
Clinical Impact: | Concomitant use of digoxin with VYTORIN may result in elevated plasma digoxin concentrations [see Clinical Pharmacology (12.3)].
Intervention: | Monitor digoxin levels in patients taking digoxin when VYTORIN is initiated.
Fenofibrates
Clinical Impact: | Both ezetimibe and fenofibrates may increase cholesterol excretion into the bile, leading to cholelithiasis.
Intervention: | If cholelithiasis is suspected in a patient receiving VYTORIN and a fenofibrate, gallbladder studies are indicated and alternative lipid-lowering therapy should be considered [see the product labeling for fenofibrate and fenofibric acid].

8 USE IN SPECIFIC POPULATIONS

8.1 Pregnancy

VYTORIN

Risk Summary

Discontinue VYTORIN when pregnancy is recognized. Alternatively, consider the ongoing therapeutic needs of the individual patient.

VYTORIN decreases synthesis of cholesterol and possibly other biologically active substances derived from cholesterol; therefore, VYTORIN may cause fetal harm when administered to pregnant patients based on the mechanism of action [see Clinical Pharmacology (12.1)]. In addition, treatment of hyperlipidemia is not generally necessary during pregnancy. Atherosclerosis is a chronic process and the discontinuation of lipid-lowering drugs during pregnancy should have little impact on the outcome of long-term therapy of primary hyperlipidemia for most patients.

Available data from case series and prospective and retrospective observational cohort studies over decades of use with statins in pregnant women have not identified a drug-associated risk of major congenital malformations. Published data from prospective and retrospective observational cohort studies with VYTORIN use in pregnant women are insufficient to determine if there is a drug-associated risk of miscarriage (see Data).

In animal reproduction studies, no adverse developmental effects were observed in pregnant rats or rabbits orally administered simvastatin during the period of organogenesis at doses that resulted in 2.5 and 2 times, respectively, the human exposure at the maximum recommended human dosage of 80 mg/day, based on body surface area (mg/m^2). In animal reproduction studies, no adverse developmental effects were observed in pregnant rats and rabbits orally administered ezetimibe during the period of organogenesis at doses that resulted in up to 10 and 150 times, respectively, the human exposure at the MRHD, based on AUC (see Data).

The estimated background risk of major birth defects and miscarriage for the indicated population is unknown. In the U.S. general population, the estimated background risk of major birth defects and miscarriage in clinically recognized pregnancies is 2 to 4% and 15 to 20%, respectively.

Data

Human Data

Ezetimibe

There are insufficient data on ezetimibe use in pregnant women to evaluate for a drug-associated risk of major birth defects, miscarriage, or adverse maternal or fetal outcomes.

Simvastatin

A Medicaid cohort linkage trial of 1152 statin-exposed pregnant women compared to 886,996 controls did not find a significant teratogenic effect from maternal use of statins in the first trimester of pregnancy, after adjusting for potential confounders – including maternal age, diabetes mellitus, hypertension, obesity, and alcohol and tobacco use – using propensity score-based methods. The relative risk of congenital malformations between the group with statin use and the group with no statin use in the first trimester was 1.07 (95% confidence interval 0.85 to 1.37) after controlling for confounders, particularly pre-existing diabetes mellitus. There were also no statistically significant increases in any of the organ-specific malformations assessed after accounting for confounders. In the majority of pregnancies, statin treatment was initiated prior to pregnancy and was discontinued at some point in the first trimester when pregnancy was identified. Trial limitations include reliance on physician coding to define the presence of a malformation, lack of control for certain confounders such as body mass index, use of prescription dispensing as verification for the use of a statin, and lack of information on non-live births.

Animal Data

Ezetimibe

In oral (gavage) embryo-fetal development studies of ezetimibe conducted in rats (gestation days 6-15) and rabbits (gestation days 7-19), there was no evidence of maternal toxicity or embryolethality at any dose tested (250, 500, 1000 mg/kg/day) at exposure equivalent to 10 to 150 times the clinical exposure, based on AUC, in rats and rabbits. In rats, increased incidences of common fetal skeletal findings (extra pair of thoracic ribs, unossified cervical vertebral centra, shortened ribs) were observed at 1000 mg/kg/day (~10 times the human exposure at 10 mg daily based on AUC0-24hr for total ezetimibe). In rabbits treated with ezetimibe, an increased incidence of extra thoracic ribs was observed at 1000 mg/kg/day (150 times the human exposure at 10 mg daily based on AUC0-24hr for total ezetimibe).

The animal-to-human exposure multiple for total ezetimibe at the no-observed effect level was 6 times for rat and 134 times for rabbit. Fetal exposure to ezetimibe (conjugated and unconjugated) was confirmed in subsequent placental transfer studies conducted using a maternal dose of 1000 mg/kg/day. The fetal maternal plasma exposure ratio (total ezetimibe) was 1.5 for rats on gestation day 20 and 0.03 for rabbits on gestation day 22.

The effect of ezetimibe on prenatal and postnatal development and maternal function was evaluated in pregnant rats at doses of 100, 300 or 1000 mg/kg/day (gestation day 6 through lactation day 21). No maternal toxicity or adverse developmental outcomes were observed up to and including the highest dose tested (17 times the human exposure at 10 mg daily based on AUC0-24hr for total ezetimibe).

Multiple-dose studies of ezetimibe given in combination with statins in rats and rabbits during organogenesis resulted in higher ezetimibe and statin exposures. Reproductive findings occurred at lower doses in combination therapy compared to monotherapy.

Simvastatin

Simvastatin was given to pregnant rats at doses of 6.25, 12.5 and 25 mg/kg/day (0.6 times, 1.3 times, and 2.5 times, respectively, the maximum recommended dosage of 80 mg/day when normalized to body surface area) from gestation days 6-17 and to pregnant rabbits from gestation days 6-18 at doses of 2.5, 5, and 10 mg/kg/day (0.5 times, 1 times, and 2 times, respectively, the maximum recommended dosage of 80 mg/day when normalized to body surface area). For both species, there was no evidence of maternal toxicity, or embryolethality. In rats, mean fetal body weights in the 25 mg/kg/day group were decreased 5.4%. Similar fetal body weight effects were not observed in rabbits.

Simvastatin doses of 6.25, 12.5 and 25 mg/kg/day (0.6 times, 1.3 times, and 2.5 times, respectively, the maximum recommended dosage of 80 mg/day when normalized to body surface area) were given to pregnant rats from gestation day 15 to lactation day 21. Slight decreases in maternal body weight gain and pup postnatal day 0 weight were observed in the 25 mg/kg/day dose group. Mean body weight gain of pups during lactation was slightly decreased at doses ≥12.5 mg/kg/day. Post weaning weight, behavior, reproductive performance and fertility of the offspring were not affected at any dose tested.

Placental transfer of simvastatin was not evaluated in rats or rabbits. However, it has been shown that other drugs in this class cross the placenta.

8.2 Lactation

Risk Summary

There is no information about the presence of ezetimibe or simvastatin in human breast milk, the effects of the drug on the breastfed infant or the effect of the drug on milk production. However, it has been shown that other statins pass into human milk. Statins, including VYTORIN, decrease cholesterol synthesis and possibly the synthesis of other biologically active substances derived from cholesterol and may cause harm to the breast fed infant.

Because of the potential for serious adverse reactions in a breastfed infant, based on the mechanism of action, advise patients that breastfeeding is not recommended during treatment with VYTORIN [see Use in Specific Populations (8.2) and Clinical Pharmacology (12.1)].

Data

Animal Data

Ezetimibe was present in the milk of lactating rats. The pup to maternal plasma ratio for total ezetimibe was 0.5 on lactation day 12.

8.4 Pediatric Use

The safety and effectiveness of ezetimibe in combination with a statin as an adjunct to diet to reduce LDL-C have been established in pediatric patients 10 years of age and older with HeFH. Use of VYTORIN for this indication is based on a double-blind, placebo-controlled clinical trial in 248 pediatric patients (142 males and 106 postmenarchal females) 10 years of age and older with HeFH [see Clinical Studies (14)]. In this limited controlled trial, there was no significant effect on growth or sexual maturation in the adolescent males or females, or on menstrual cycle length in females.

The safety and effectiveness of VYTORIN have not been established in pediatric patients younger than 10 years of age with HeFH, or in pediatric patients with other types of hyperlipidemia.

8.5 Geriatric Use

Advanced age (≥65 years) is a risk factor for VYTORIN-associated myopathy and rhabdomyolysis. Dose selection for an elderly patient should be cautious, recognizing the greater frequency of decreased hepatic, renal, or cardiac function, and of concomitant disease or other drug therapy and the higher risk of myopathy. Monitor geriatric patients receiving VYTORIN for the increased risk of myopathy [see Warnings and Precautions (5.1)].

Of the 10,189 patients who received VYTORIN in clinical studies, 3242 (32%) were 65 and older (this included 844 (8%) who were 75 and older). No overall differences in safety or effectiveness were observed between these subjects and younger subjects, and other reported clinical experience has not identified differences in responses between the elderly and younger patients but greater sensitivity of some older individuals cannot be ruled out.

8.6 Renal Impairment

Renal impairment is a risk factor for myopathy and rhabdomyolysis. Monitor all patients with renal impairment for development of myopathy. Doses of VYTORIN exceeding 10/20 mg should be used with caution and close monitoring in patients with moderate to severe renal impairment [see Dosage and Administration (2.4) and Warnings and Precautions (5.1)].

In the SHARP trial of 9270 patients with moderate to severe renal impairment (6247 non-dialysis patients with median serum creatinine 2.5 mg/dL and median estimated glomerular filtration rate 25.6 mL/min/1.73 m^2, and 3023 dialysis patients), the incidence of serious adverse events, adverse events leading to discontinuation of trial treatment, or adverse events of special interest (musculoskeletal adverse events, liver enzyme abnormalities, incident cancer) was similar between patients ever assigned to VYTORIN 10/20 mg (n=4650) or placebo (n=4620) during a median follow-up of 4.9 years.

8.7 Hepatic Impairment

VYTORIN is contraindicated in patients with acute liver failure or decompensated cirrhosis. [See Contraindications (4) and Warnings and Precautions (5.3).]

8.8 Chinese Patients

In a clinical trial in which patients at high risk of CVD were treated with simvastatin 40 mg/day (median follow-up 3.9 years), the incidence of myopathy was approximately 0.05% for non-Chinese patients (n=7367) compared with 0.24% for Chinese patients (n=5468). In this trial the incidence of myopathy for Chinese patients on simvastatin 40 mg/day or ezetimibe and simvastatin 10/40 mg/day coadministered with extended-release niacin 2 g/day was 1.24%.

Chinese patients may be at higher risk for myopathy, monitor these patients appropriately. Coadministration of VYTORIN with lipid-modifying doses of niacin-containing products (≥1 g/day niacin) is not recommended in Chinese patients [see Warnings and Precautions (5.1) and Drug Interactions (7.1)].

10 OVERDOSAGE

No specific antidotes for VYTORIN are known. In the event of an overdose with VYTORIN, consider contacting the Poison Help Line (1-800-222-1222) or a medical toxicologist for overdosage management recommendations.

11 DESCRIPTION

VYTORIN contains ezetimibe, a dietary cholesterol absorption inhibitor, and simvastatin, an HMG CoA reductase inhibitor.

The chemical name of ezetimibe is 1-(4-fluorophenyl)-3(R)-[3-(4-fluorophenyl)-3(S)-hydroxypropyl]-4(S)-(4-hydroxyphenyl)-2-azetidinone. The empirical formula is C24H21F2NO3 and its molecular weight is 409.4.

Ezetimibe is a white, crystalline powder that is freely to very soluble in ethanol, methanol, and acetone and practically insoluble in water. Its structural formula is:

Simvastatin, an inactive lactone, is hydrolyzed to the corresponding β-hydroxyacid form, which is an inhibitor of HMG-CoA reductase. Simvastatin is butanoic acid, 2,2-dimethyl-,1,2,3,7,8,8a-hexahydro-3,7-dimethyl-8-[2-(tetrahydro-4-hydroxy-6-oxo-2H-pyran-2-yl)-ethyl]-1-naphthalenyl ester, [1S-[1α,3α,7β,8β(2S*,4S*),-8aβ]]. The empirical formula of simvastatin is C25H38O5 and its molecular weight is 418.57.

Simvastatin is a white to off-white, nonhygroscopic, crystalline powder that is practically insoluble in water and freely soluble in chloroform, methanol and ethanol. Its structural formula is:

VYTORIN is available for oral use as tablets containing 10 mg of ezetimibe, and 10 mg of simvastatin (VYTORIN 10/10), 20 mg of simvastatin (VYTORIN 10/20), 40 mg of simvastatin (VYTORIN 10/40), or 80 mg of simvastatin (VYTORIN 10/80). Each tablet contains the following inactive ingredients: butylated hydroxyanisole NF, citric acid monohydrate USP, croscarmellose sodium NF, hypromellose USP, lactose monohydrate NF, magnesium stearate NF, microcrystalline cellulose NF, and propyl gallate NF.

12 CLINICAL PHARMACOLOGY

12.1 Mechanism of Action

VYTORIN

Plasma cholesterol is derived from intestinal absorption and endogenous synthesis. VYTORIN contains ezetimibe and simvastatin, two lipid-lowering compounds with complementary mechanisms of action.

Ezetimibe

Ezetimibe reduces blood cholesterol by inhibiting the absorption of cholesterol by the small intestine. The molecular target of ezetimibe has been shown to be the sterol transporter, Niemann-Pick C1-Like 1 (NPC1L1), which is involved in the intestinal uptake of cholesterol and phytosterols.

Ezetimibe localizes at the brush border of the small intestine and inhibits the absorption of cholesterol, leading to a decrease in the delivery of intestinal cholesterol to the liver. This causes a reduction of hepatic cholesterol stores and an increase in clearance of cholesterol from the blood.

Simvastatin

Simvastatin is a prodrug and is hydrolyzed to its active β-hydroxyacid form, simvastatin acid, after administration. Simvastatin acid and its metabolites are inhibitors of HMG-CoA reductase, the rate-limiting enzyme converts HMG-CoA to mevalonate, a precursor of cholesterol.

12.2 Pharmacodynamics

VYTORIN reduces total cholesterol (total-C), LDL-C, apolipoprotein (Apo) B, and non-high-density lipoprotein cholesterol (non-HDL-C) in patients with hyperlipidemia.

Ezetimibe

In a 2-week clinical trial in 18 hypercholesterolemic patients, ezetimibe inhibited intestinal cholesterol absorption by 54%, compared with placebo. Ezetimibe had no clinically meaningful effect on the plasma concentrations of the fat-soluble vitamins A, D, and E and did not impair adrenocortical steroid hormone production.

Simvastatin

Inhibition of HMG-CoA reductase by simvastatin acid accelerates the expression of LDL-receptors, followed by the uptake of LDL-C from blood to the liver, leading to a decrease in plasma LDL-C and total cholesterol. Sustained inhibition of cholesterol synthesis in the liver also decreases levels of very-low density lipoproteins. The maximum LDL-C reduction of ZOCOR is usually achieved by 4 weeks and is maintained after that.

12.3 Pharmacokinetics

The results of a bioequivalence trial in healthy subjects demonstrated that the VYTORIN (ezetimibe and simvastatin) 10 mg/10 mg to 10 mg/80 mg combination tablets are bioequivalent to coadministration of corresponding doses of ezetimibe (ZETIA®) and simvastatin (ZOCOR®) as individual tablets.

Absorption

Ezetimibe

After oral administration, ezetimibe is absorbed and extensively conjugated to a pharmacologically active phenolic glucuronide (ezetimibe-glucuronide). Mean maximum plasma concentrations (Cmax) occur within 1 to 2 hours for ezetimibe-glucuronide and 4 to 12 hours for ezetimibe. The absolute bioavailability of ezetimibe cannot be determined as the compound is virtually insoluble in aqueous media suitable for injection.

Simvastatin

The availability of the β-hydroxyacid to the systemic circulation following an oral dose of simvastatin was found to be less than 5% of the dose, consistent with extensive hepatic first-pass extraction.

Effect of Food on Oral Absorption

Ezetimibe

Concomitant food administration (high-fat or non-fat meals) had no effect on the extent of absorption of ezetimibe when administered as 10-mg tablets. The Cmax value of ezetimibe was increased by 38% with consumption of high-fat meals.

Simvastatin

Relative to the fasting state, the plasma profiles of both active and total inhibitors of HMG-CoA reductase were not affected when simvastatin was administered immediately before an American Heart Association recommended low-fat meal.

Distribution

Ezetimibe

Ezetimibe and ezetimibe-glucuronide are highly bound (>90%) to human plasma proteins.

Simvastatin

Both simvastatin and its β-hydroxyacid metabolite are highly bound (approximately 95%) to human plasma proteins. When radiolabeled simvastatin was administered to rats, simvastatin-derived radioactivity crossed the blood-brain barrier.

Elimination

Metabolism

Ezetimibe

Ezetimibe is primarily metabolized in the small intestine and liver via glucuronide conjugation with subsequent biliary and renal excretion. Minimal oxidative metabolism has been observed in all species evaluated.

In humans, ezetimibe is rapidly metabolized to ezetimibe-glucuronide. Ezetimibe and ezetimibe-glucuronide are the major drug-derived compounds detected in plasma, constituting approximately 10 to 20% and 80 to 90% of the total drug in plasma, respectively. Both ezetimibe and ezetimibe-glucuronide are eliminated from plasma with a half-life of approximately 22 hours for both ezetimibe and ezetimibe-glucuronide. Plasma concentration-time profiles exhibit multiple peaks, suggesting enterohepatic recycling.

Simvastatin

Simvastatin is a lactone that is readily hydrolyzed in vivo to the corresponding β-hydroxyacid, a potent inhibitor of HMG-CoA reductase. Inhibition of HMG-CoA reductase is a basis for an assay in pharmacokinetic studies of the β-hydroxyacid metabolites (active inhibitors) and, following base hydrolysis, active plus latent inhibitors (total inhibitors) in plasma following administration of simvastatin. The major active metabolites of simvastatin present in human plasma are the β-hydroxyacid of simvastatin and its 6'-hydroxy, 6'-hydroxymethyl, and 6'-exomethylene derivatives.

Excretion

Ezetimibe

Following oral administration of ^14C-ezetimibe (20 mg) to human subjects, total ezetimibe (ezetimibe + ezetimibe-glucuronide) accounted for approximately 93% of the total radioactivity in plasma. After 48 hours, there were no detectable levels of radioactivity in the plasma.

Approximately 78% and 11% of the administered radioactivity were recovered in the feces and urine, respectively, over a 10-day collection period. Ezetimibe was the major component in feces and accounted for 69% of the administered dose, while ezetimibe-glucuronide was the major component in urine and accounted for 9% of the administered dose.

Simvastatin

Following an oral dose of ^14C-labeled simvastatin in man, 13% of the dose was excreted in urine and 60% in feces. Plasma concentrations of total radioactivity (simvastatin plus ^14C-metabolites) peaked at 4 hours and declined rapidly to about 10% of peak by 12 hours postdose.

Specific Populations

Geriatric Patients

Ezetimibe

In a multiple-dose trial with ezetimibe given 10 mg once daily for 10 days, plasma concentrations for total ezetimibe were about 2-fold higher in older (≥65 years) healthy subjects compared to younger subjects.

Simvastatin

In a trial including 16 geriatric patients between 70 and 78 years of age who received simvastatin 40 mg/day, the mean plasma level of total inhibitors activity was increased approximately 45% compared with 18 patients between 18-30 years of age. [See Use in Specific Populations (8.5).]

Gender

Ezetimibe

In a multiple-dose trial with ezetimibe given 10 mg once daily for 10 days, plasma concentrations for total ezetimibe were slightly higher (<20%) in females than in males.

Race

Ezetimibe

Based on a meta-analysis of multiple-dose pharmacokinetic studies, there were no pharmacokinetic differences between Black or African American and White subjects. Studies in Asian subjects indicated that the pharmacokinetics of ezetimibe was similar to those seen in White subjects.

Hepatic Impairment

Ezetimibe

After a single 10-mg dose of ezetimibe, the mean exposure (based on area under the curve [AUC]) to total ezetimibe was increased approximately 1.7-fold in patients with mild hepatic impairment (Child-Pugh score 5 to 6), compared to healthy subjects. The mean AUC values for total ezetimibe and ezetimibe increased approximately 3- to 4-fold and 5- to 6-fold, respectively, in patients with moderate (Child-Pugh score 7 to 9) or severe hepatic impairment (Child-Pugh score 10 to 15). In a 14-day, multiple-dose trial (10 mg daily) in patients with moderate hepatic impairment, the mean AUC for total ezetimibe and ezetimibe increased approximately 4-fold compared to healthy subjects.

Renal Impairment

Ezetimibe

After a single 10-mg dose of ezetimibe in patients with severe renal disease (n=8; mean CrCl ≤30 mL/min/1.73 m^2), the mean AUC for total ezetimibe and ezetimibe increased approximately 1.5-fold, compared to healthy subjects (n=9).

Simvastatin

Pharmacokinetic studies with another statin having a similar principal route of elimination to that of simvastatin have suggested that for a given dose level higher systemic exposure may be achieved in patients with severe renal impairment (as measured by creatinine clearance).

Drug Interactions [See also Drug Interactions (7).]

No clinically significant pharmacokinetic interaction was seen when ezetimibe was coadministered with simvastatin. No specific pharmacokinetic drug interaction studies with VYTORIN have been conducted other than the following trial with NIASPAN (Niacin extended-release tablets).

Niacin: The effect of VYTORIN (10/20 mg daily for 7 days) on the pharmacokinetics of NIASPAN extended-release tablets (1000 mg for 2 days and 2000 mg for 5 days following a low-fat breakfast) was studied in healthy subjects. The mean Cmax and AUC of niacin increased 9% and 22%, respectively. The mean Cmax and AUC of nicotinuric acid increased 10% and 19%, respectively (N=13). In the same trial, the effect of NIASPAN on the pharmacokinetics of VYTORIN was evaluated (N=15). While concomitant NIASPAN decreased the mean Cmax of total ezetimibe (1%), and simvastatin (2%), it increased the mean Cmax of simvastatin acid (18%). In addition, concomitant NIASPAN increased the mean AUC of total ezetimibe (26%), simvastatin (20%), and simvastatin acid (35%).

Cases of myopathy/rhabdomyolysis have been observed with simvastatin coadministered with lipid-modifying doses (≥1 g/day niacin) of niacin-containing products. [See Warnings and Precautions (5.1) and Drug Interactions (7.1).]

Cytochrome P450: Ezetimibe had no significant effect on a series of probe drugs (caffeine, dextromethorphan, tolbutamide, and IV midazolam) known to be metabolized by cytochrome P450 (1A2, 2D6, 2C8/9 and 3A4) in a “cocktail” trial of twelve healthy adult males. This indicates that ezetimibe is neither an inhibitor nor an inducer of these cytochrome P450 isozymes, and it is unlikely that ezetimibe will affect the metabolism of drugs that are metabolized by these enzymes.

In a trial of 12 healthy volunteers, simvastatin at the 80-mg dose had no effect on the metabolism of the probe cytochrome P450 isoform 3A4 (CYP3A4) substrates midazolam and erythromycin. This indicates that simvastatin is not an inhibitor of CYP3A4 and, therefore, is not expected to affect the plasma levels of other drugs metabolized by CYP3A4.

Simvastatin acid is a substrate of the transport protein OATP1B1. Concomitant administration of medicinal products that are inhibitors of the transport protein OATP1B1 may lead to increased plasma concentrations of simvastatin acid and an increased risk of myopathy. For example, cyclosporine has been shown to increase the AUC of statins; although the mechanism is not fully understood, the increase in AUC for simvastatin acid is presumably due, in part, to inhibition of CYP3A4 and/or OATP1B1 [see Drug Interactions (7)].

Simvastatin is a substrate for CYP3A4. Inhibitors of CYP3A4 can raise the plasma levels of HMG-CoA reductase inhibitory activity and increase the risk of myopathy. [See Warnings and Precautions (5.1) and Drug Interactions (7.1).]

Ezetimibe

Table 5 displays the effect of coadministered drugs on total ezetimibe.

Table 5: Effect of Coadministered Drugs on Total Ezetimibe
Coadministered Drug and Dosing Regimen | Total Ezetimibe [Based on 10 mg-dose of ezetimibe.]
 | Change in AUC | Change in Cmax
Cyclosporine-stable dose required (75-150 mg BID) [Post-renal transplant patients with mild impaired or normal renal function. In a different trial, a renal transplant patient with severe renal insufficiency (creatinine clearance of 13.2 mL/min/1.73 m^2) who was receiving multiple medications, including cyclosporine, demonstrated a 12-fold greater exposure to total ezetimibe compared to healthy subjects.] , [See 7. Drug Interactions.] | ↑240% | ↑290%
Fenofibrate, 200 mg QD, 14 days | ↑48% | ↑64%
Gemfibrozil, 600 mg BID, 7 days | ↑64% | ↑91%
Cholestyramine, 4 g BID, 14 days | ↓55% | ↓4%
Aluminum & magnesium hydroxide combination antacid, single dose [Supralox, 20 mL.] | ↓4% | ↓30%
Cimetidine, 400 mg BID, 7 days | ↑6% | ↑22%
Glipizide, 10 mg, single dose | ↑4% | ↓8%
Statins
Lovastatin 20 mg QD, 7 days | ↑9% | ↑3%
Pravastatin 20 mg QD, 14 days | ↑7% | ↑23%
Atorvastatin 10 mg QD, 14 days | ↓2% | ↑12%
Rosuvastatin 10 mg QD, 14 days | ↑13% | ↑18%
Fluvastatin 20 mg QD, 14 days | ↓19% | ↑7%

Table 6 displays the effects of ezetimibe coadministration on systemic exposure to other drugs.

Table 6: Effect of Ezetimibe Coadministration on Systemic Exposure to Other Drugs
Coadministered Drug and its Dosage Regimen | Ezetimibe Dosage Regimen | Change in AUC of Coadministered Drug | Change in Cmax of Coadministered Drug
Warfarin, 25 mg single dose on Day 7 | 10 mg QD, 11 days | ↓2% (R-warfarin) ↓4% (S-warfarin) | ↑3% (R-warfarin) ↑1% (S-warfarin)
Digoxin, 0.5 mg single dose | 10 mg QD, 8 days | ↑2% | ↓7%
Gemfibrozil, 600 mg BID, 7 days [See 7. Drug Interactions.] | 10 mg QD, 7 days | ↓1% | ↓11%
Ethinyl estradiol & Levonorgestrel, QD, 21 days | 10 mg QD, Days 8-14 of 21 day oral contraceptive cycle | Ethinyl estradiol 0% Levonorgestrel 0% | Ethinyl estradiol ↓9% Levonorgestrel ↓5%
Glipizide, 10 mg on Days 1 and 9 | 10 mg QD, Days 2-9 | ↓3% | ↓5%
Fenofibrate, 200 mg QD, 14 days | 10 mg QD, 14 days | ↑11% | ↑7%
Cyclosporine, 100 mg single dose Day 7 | 20 mg QD, 8 days | ↑15% | ↑10%
Statins
Lovastatin 20 mg QD, 7 days | 10 mg QD, 7 days | ↑19% | ↑3%
Pravastatin 20 mg QD, 14 days | 10 mg QD, 14 days | ↓20% | ↓24%
Atorvastatin 10 mg QD, 14 days | 10 mg QD, 14 days | ↓4% | ↑7%
Rosuvastatin 10 mg QD, 14 days | 10 mg QD, 14 days | ↑19% | ↑17%
Fluvastatin 20 mg QD, 14 days | 10 mg QD, 14 days | ↓39% | ↓27%

Simvastatin

Table 7 displays the effects of coadminstration drugs or grapefruit juice on simvastatin systemic exposure [see Drug Interactions (7)].

Table 7: Effect of Coadministered Drugs or Grapefruit Juice on Simvastatin Systemic Exposure
Coadministered Drug or Grapefruit Juice | Dosing of Coadministered Drug or Grapefruit Juice | Dosing of Simvastatin | Geometric Mean Ratio (Ratio [Results based on a chemical assay except results with propranolol as indicated.] with / without coadministered drug) No Effect = 1.00
Coadministered Drug or Grapefruit Juice | Dosing of Coadministered Drug or Grapefruit Juice | Dosing of Simvastatin |  | AUC | Cmax
Telithromycin [Results could be representative of the following CYP3A4 inhibitors: ketoconazole, erythromycin, clarithromycin, HIV protease inhibitors, and nefazodone.] | 200 mg QD for 4 days | 80 mg | simvastatin acid [Simvastatin acid refers to the β-hydroxyacid of simvastatin.] | 12 | 15
 |  |  | simvastatin | 8.9 | 5.3
Nelfinavir | 1250 mg BID for 14 days | 20 mg QD for 28 days | simvastatin acid
 |  |  | simvastatin | 6 | 6.2
Itraconazole | 200 mg QD for 4 days | 80 mg | simvastatin acid |  | 13.1
 |  |  | simvastatin |  | 13.1
Posaconazole | 100 mg (oral suspension) QD for 13 days | 40 mg | simvastatin acid | 7.3 | 9.2
 | 100 mg (oral suspension) QD for 13 days |  | simvastatin | 10.3 | 9.4
 | 200 mg (oral suspension) QD for 13 days | 40 mg | simvastatin acid | 8.5 | 9.5
 | 200 mg (oral suspension) QD for 13 days |  | simvastatin | 10.6 | 11.4
Gemfibrozil | 600 mg BID for 3 days | 40 mg | simvastatin acid | 2.85 | 2.18
 |  |  | simvastatin | 1.35 | 0.91
Grapefruit Juice [The effect of amounts of grapefruit juice between those used in these two studies on simvastatin pharmacokinetics has not been studied.] (high dose) | 200 mL of double-strength TID [Double-strength: one can of frozen concentrate diluted with one can of water. Grapefruit juice was administered TID for 2 days, and 200 mL together with single dose simvastatin and 30 and 90 minutes following single dose simvastatin on Day 3.] | 60 mg single dose | simvastatin acid | 7
 |  |  | simvastatin | 16
Grapefruit Juice (low dose) | 8 oz (about 237 mL) of single-strength [Single-strength: one can of frozen concentrate diluted with 3 cans of water. Grapefruit juice was administered with breakfast for 3 days, and simvastatin was administered in the evening on Day 3.] | 20 mg single dose | simvastatin acid | 1.3
 |  |  | simvastatin | 1.9
Verapamil SR | 240 mg QD Days 1-7 then 240 mg BID on Days 8-10 | 80 mg on Day 10 | simvastatin acid | 2.3 | 2.4
 | 240 mg QD Days 1-7 then 240 mg BID on Days 8-10 |  | simvastatin | 2.5 | 2.1
Diltiazem | 120 mg BID for 10 days | 80 mg on Day 10 | simvastatin acid | 2.69 | 2.69
 |  |  | simvastatin | 3.10 | 2.88
Diltiazem | 120 mg BID for 14 days | 20 mg on Day 14 | simvastatin | 4.6 | 3.6
Dronedarone | 400 mg BID for 14 days | 40 mg QD for 14 days | simvastatin acid | 1.96 | 2.14
 |  |  | simvastatin | 3.90 | 3.75
Amiodarone | 400 mg QD for 3 days | 40 mg on Day 3 | simvastatin acid | 1.75 | 1.72
 |  |  | simvastatin | 1.76 | 1.79
Amlodipine | 10 mg QD for 10 days | 80 mg on Day 10 | simvastatin acid | 1.58 | 1.56
 |  |  | simvastatin | 1.77 | 1.47
Ranolazine SR | 1000 mg BID for 7 days | 80 mg on Day 1 and Days 6-9 | simvastatin acid | 2.26 | 2.28
 |  |  | simvastatin | 1.86 | 1.75
Lomitapide | 60 mg QD for 7 days | 40 mg single dose | simvastatin acid | 1.7 | 1.6
 |  |  | simvastatin | 2 | 2
Lomitapide | 10 mg QD for 7 days | 20 mg single dose | simvastatin acid | 1.4 | 1.4
 |  |  | simvastatin | 1.6 | 1.7
Fenofibrate | 160 mg QD for 14 days | 80 mg QD on Days 8-14 | simvastatin acid | 0.64 | 0.89
 |  |  | simvastatin | 0.89 | 0.83
Propranolol | 80 mg single dose | 80 mg single dose | total inhibitor | 0.79 | ↓ from 33.6 to 21.1 ng∙eq/mL
 |  |  | active inhibitor | 0.79 | ↓ from 7.0 to 4.7 ng∙eq/mL

13 NONCLINICAL TOXICOLOGY

13.1 Carcinogenesis, Mutagenesis, Impairment of Fertility

VYTORIN

No animal carcinogenicity or fertility studies have been conducted with the combination of ezetimibe and simvastatin. The combination of ezetimibe with simvastatin did not show evidence of mutagenicity in vitro in a microbial mutagenicity (Ames) test with Salmonella typhimurium and Escherichia coli with or without metabolic activation. No evidence of clastogenicity was observed in vitro in a chromosomal aberration assay in human peripheral blood lymphocytes with ezetimibe and simvastatin with or without metabolic activation. There was no evidence of genotoxicity at doses up to 600 mg/kg with the combination of ezetimibe and simvastatin (1:1) in the in vivo mouse micronucleus test.

Ezetimibe

A 104-week dietary carcinogenicity trial with ezetimibe was conducted in rats at doses up to 1500 mg/kg/day (males) and 500 mg/kg/day (females) (~20 times the human exposure at 10 mg daily based on AUC0-24hr for total ezetimibe). A 104-week dietary carcinogenicity trial with ezetimibe was also conducted in mice at doses up to 500 mg/kg/day (>150 times the human exposure at 10 mg daily based on AUC0-24hr for total ezetimibe). There were no statistically significant increases in tumor incidences in drug-treated rats or mice.

No evidence of mutagenicity was observed in vitro in a microbial mutagenicity (Ames) test with Salmonella typhimurium and Escherichia coli with or without metabolic activation. No evidence of clastogenicity was observed in vitro in a chromosomal aberration assay in human peripheral blood lymphocytes with or without metabolic activation. In addition, there was no evidence of genotoxicity in the in vivo mouse micronucleus test.

In oral (gavage) fertility studies of ezetimibe conducted in rats, there was no evidence of reproductive toxicity at doses up to 1000 mg/kg/day in male or female rats (~7 times the human exposure at 10 mg daily based on AUC0-24hr for total ezetimibe).

Simvastatin

In a 72-week carcinogenicity trial, mice were administered daily doses of simvastatin of 25, 100, and 400 mg/kg body weight, which resulted in mean plasma drug levels approximately 1, 4, and 8 times higher than the mean human plasma drug level, respectively, (as total inhibitory activity based on AUC) after an 80-mg oral dose. Liver carcinomas were significantly increased in high-dose females and mid- and high-dose males with a maximum incidence of 90% in males. The incidence of adenomas of the liver was significantly increased in mid- and high-dose females. Drug treatment also significantly increased the incidence of lung adenomas in mid- and high-dose males and females. Adenomas of the Harderian gland (a gland of the eye of rodents) were significantly higher in high-dose mice than in controls. No evidence of a tumorigenic effect was observed at 25 mg/kg/day.

In a separate 92-week carcinogenicity trial in mice at doses up to 25 mg/kg/day, no evidence of a tumorigenic effect was observed (mean plasma drug levels were 1 times higher than humans given 80 mg simvastatin as measured by AUC).

In a two-year trial in rats at 25 mg/kg/day, there was a statistically significant increase in the incidence of thyroid follicular adenomas in female rats exposed to approximately 11 times higher levels of simvastatin than in humans given 80 mg simvastatin (as measured by AUC).

A second two-year rat carcinogenicity trial with doses of 50 and 100 mg/kg/day produced hepatocellular adenomas and carcinomas (in female rats at both doses and in males at 100 mg/kg/day). Thyroid follicular cell adenomas were increased in males and females at both doses; thyroid follicular cell carcinomas were increased in females at 100 mg/kg/day. The increased incidence of thyroid neoplasms appears to be consistent with findings from other statins. These treatment levels represented plasma drug levels (AUC) of approximately 7 and 15 times (males) and 22 and 25 times (females) the mean human plasma drug exposure after an 80-mg daily dose.

No evidence of mutagenicity was observed in a microbial mutagenicity (Ames) test with or without rat or mouse liver metabolic activation. In addition, no evidence of damage to genetic material was noted in an in vitro alkaline elution assay using rat hepatocytes, a V-79 mammalian cell forward mutation trial, an in vitro chromosome aberration trial in CHO cells, or an in vivo chromosomal aberration assay in mouse bone marrow.

There was decreased fertility in male rats treated with simvastatin for 34 weeks at 25 mg/kg body weight (4 times the maximum human exposure level, based on AUC, in patients receiving 80 mg/day); however, this effect was not observed during a subsequent fertility trial in which simvastatin was administered at this same dose level to male rats for 11 weeks (the entire cycle of spermatogenesis including epididymal maturation). No microscopic changes were observed in the testes of rats from either trial. At 180 mg/kg/day (which produces exposure levels 22 times higher than those in humans taking 80 mg/day based on surface area, mg/m^2), seminiferous tubule degeneration (necrosis and loss of spermatogenic epithelium) was observed. In dogs, there was drug-related testicular atrophy, decreased spermatogenesis, spermatocytic degeneration and giant cell formation at 10 mg/kg/day (approximately 2 times the human exposure, based on AUC, at 80 mg/day). The clinical significance of these findings is unclear.

14 CLINICAL STUDIES

Primary Hyperlipidemia in Adults

VYTORIN

VYTORIN reduces LDL-C in adult patients with primary hyperlipidemia. Maximal to near maximal response is generally achieved within 2 weeks and maintained during chronic therapy.

VYTORIN is effective in males and females with primary hyperlipidemia. There were insufficient numbers of patients who self-identified as Black or African American, Asian, or other races to determine if these patients responded differently than White patients.

Five multicenter, double-blind trials conducted with either VYTORIN or coadministered ezetimibe and simvastatin equivalent to VYTORIN in patients with primary hyperlipidemia are reported: two were comparisons with simvastatin, two were comparisons with atorvastatin, and one was a comparison with rosuvastatin.

In a multicenter, double-blind, placebo-controlled, 12-week trial, 1528 patients with primary hyperlipidemia were randomized to one of ten treatment groups: placebo, ezetimibe (10 mg), simvastatin (10 mg, 20 mg, 40 mg, or 80 mg), or VYTORIN (10/10, 10/20, 10/40, or 10/80).

When patients receiving VYTORIN were compared to those receiving all doses of simvastatin, VYTORIN significantly lowered total-C, LDL-C, Apo B, TG, and non-HDL-C. The effects of VYTORIN on HDL-C were similar to the effects seen with simvastatin. Further analysis showed VYTORIN significantly increased HDL-C compared with placebo. (See Table 8.) The lipid response to VYTORIN was similar in patients with TG levels greater than or less than 200 mg/dL.

Table 8: Response to VYTORIN in Patients with Primary Hyperlipidemia (Mean [For triglycerides, median % change from baseline.] % Change from Untreated Baseline [Baseline - on no lipid-lowering drug.])
Treatment
(Daily Dose) | N | Total-C | LDL-C | Apo B | HDL-C | TG | Non-HDL-C
Pooled data (All VYTORIN doses) [VYTORIN doses pooled (10/10-10/80) significantly reduced total-C, LDL-C, Apo B, TG, and non-HDL-C compared to simvastatin and significantly increased HDL-C compared to placebo.] | 609 | -38 | -53 | -42 | +7 | -24 | -49
Pooled data (All simvastatin doses) | 622 | -28 | -39 | -32 | +7 | -21 | -36
Ezetimibe 10 mg | 149 | -13 | -19 | -15 | +5 | -11 | -18
Placebo | 148 | -1 | -2 | 0 | 0 | -2 | -2
VYTORIN by dose
10/10 | 152 | -31 | -45 | -35 | +8 | -23 | -41
10/20 | 156 | -36 | -52 | -41 | +10 | -24 | -47
10/40 | 147 | -39 | -55 | -44 | +6 | -23 | -51
10/80 | 154 | -43 | -60 | -49 | +6 | -31 | -56
Simvastatin by dose
10 mg | 158 | -23 | -33 | -26 | +5 | -17 | -30
20 mg | 150 | -24 | -34 | -28 | +7 | -18 | -32
40 mg | 156 | -29 | -41 | -33 | +8 | -21 | -38
80 mg | 158 | -35 | -49 | -39 | +7 | -27 | -45

In a multicenter, double-blind, controlled, 23-week trial, 710 patients with known CHD or CHD risk equivalents, as defined by the NCEP ATP III guidelines, and an LDL-C ≥130 mg/dL were randomized to one of four treatment groups: coadministered ezetimibe and simvastatin equivalent to VYTORIN (10/10, 10/20, and 10/40) or simvastatin 20 mg. Patients not reaching an LDL-C <100 mg/dL had their simvastatin dose titrated at 6-week intervals to a maximal dose of 80 mg. At Week 5, the LDL-C reductions with VYTORIN 10/10, 10/20, or 10/40 were significantly larger than with simvastatin 20 mg (see Table 9).

Table 9: Response to VYTORIN after 5 Weeks in Patients with CHD or CHD Risk Equivalents and an LDL-C ≥130 mg/dL
 | Simvastatin 20 mg | VYTORIN 10/10 | VYTORIN 10/20 | VYTORIN 10/40
N | 253 | 251 | 109 | 97
Mean baseline LDL-C | 174 | 165 | 167 | 171
Percent change LDL-C | -38 | -47 | -53 | -59

In a multicenter, double-blind, 6-week trial, 1902 patients with primary hyperlipidemia were randomized to one of eight treatment groups: VYTORIN (10/10, 10/20, 10/40, or 10/80) or atorvastatin (10 mg, 20 mg, 40 mg, or 80 mg).

Across the dosage range, when patients receiving VYTORIN were compared to those receiving milligram-equivalent statin doses of atorvastatin, VYTORIN lowered total-C, LDL-C, Apo B, and non-HDL-C significantly more than atorvastatin. Only the 10/40 mg and 10/80 mg VYTORIN doses increased HDL-C significantly more than the corresponding milligram-equivalent statin dose of atorvastatin. The effects of VYTORIN on TG were similar to the effects seen with atorvastatin. (See Table 10.)

Table 10: Response to VYTORIN and Atorvastatin in Patients with Primary Hyperlipidemia (Mean [For triglycerides, median % change from baseline.] % Change from Untreated Baseline [Baseline - on no lipid-lowering drug.])
Treatment
(Daily Dose) | N | Total-C [VYTORIN doses pooled (10/10-10/80) provided significantly greater reductions in total-C, LDL-C, Apo B, and non-HDL-C compared to atorvastatin doses pooled (10-80).] | LDL-C | Apo B | HDL-C | TG | Non-HDL-C
VYTORIN by dose
10/10 | 230 | -34 [p<0.05 for difference with atorvastatin at equal mg doses of the simvastatin component.] | -47 | -37 | +8 | -26 | -43
10/20 | 233 | -37 | -51 | -40 | +7 | -25 | -46
10/40 | 236 | -41 | -57 | -46 | +9 | -27 | -52
10/80 | 224 | -43 | -59 | -48 | +8 | -31 | -54
Atorvastatin by dose
10 mg | 235 | -27 | -36 | -31 | +7 | -21 | -34
20 mg | 230 | -32 | -44 | -37 | +5 | -25 | -41
40 mg | 232 | -36 | -48 | -40 | +4 | -24 | -45
80 mg | 230 | -40 | -53 | -44 | +1 | -32 | -50

In a multicenter, double-blind, 24-week, forced-titration trial, 788 patients with primary hyperlipidemia were randomized to receive coadministered ezetimibe and simvastatin equivalent to VYTORIN (10/10 and 10/20) or atorvastatin 10 mg. For all three treatment groups, the dose of the statin was titrated at 6-week intervals to 80 mg. At each pre-specified dose comparison, VYTORIN lowered LDL-C to a greater degree than atorvastatin (see Table 11).

Table 11: Response to VYTORIN and Atorvastatin in Patients with Primary Hyperlipidemia (Mean [For triglycerides, median % change from baseline.] % Change from Untreated Baseline [Baseline - on no lipid-lowering drug.])
Treatment | N | Total-C | LDL-C | Apo B | HDL-C | TG | Non-HDL-C
Week 6
Atorvastatin 10 mg [Atorvastatin: 10 mg start dose titrated to 20 mg, 40 mg, and 80 mg through Weeks 6, 12, 18, and 24.] | 262 | -28 | -37 | -32 | +5 | -23 | -35
VYTORIN 10/10 [VYTORIN: 10/10 start dose titrated to 10/20, 10/40, and 10/80 through Weeks 6, 12, 18, and 24.] | 263 | -34 [p≤0.05 for difference with atorvastatin in the specified week.] | -46 | -38 | +8 | -26 | -43
VYTORIN 10/20 [VYTORIN: 10/20 start dose titrated to 10/40, 10/40, and 10/80 through Weeks 6, 12, 18, and 24.] | 263 | -36 | -50 | -41 | +10 | -25 | -46
Week 12
Atorvastatin 20 mg | 246 | -33 | -44 | -38 | +7 | -28 | -42
VYTORIN 10/20 | 250 | -37 | -50 | -41 | +9 | -28 | -46
VYTORIN 10/40 | 252 | -39 | -54 | -45 | +12 | -31 | -50
Week 18
Atorvastatin 40 mg | 237 | -37 | -49 | -42 | +8 | -31 | -47
VYTORIN 10/40 [Data pooled for common doses of VYTORIN at Weeks 18 and 24.] | 482 | -40 | -56 | -45 | +11 | -32 | -52
Week 24
Atorvastatin 80 mg | 228 | -40 | -53 | -45 | +6 | -35 | -50
VYTORIN 10/80 | 459 | -43 | -59 | -49 | +12 | -35 | -55

In a multicenter, double-blind, 6-week trial, 2959 patients with primary hyperlipidemia, were randomized to one of six treatment groups: VYTORIN (10/20, 10/40, or 10/80) or rosuvastatin (10 mg, 20 mg, or 40 mg).

The effects of VYTORIN and rosuvastatin on total-C, LDL-C, Apo B, TG, non-HDL-C and HDL-C are shown in Table 12.

Table 12: Response to VYTORIN and Rosuvastatin in Patients with Primary Hyperlipidemia (Mean [For triglycerides, median % change from baseline.] % Change from Untreated Baseline [Baseline - on no lipid-lowering drug.])
Treatment
(Daily Dose) | N | Total-C [VYTORIN doses pooled (10/20-10/80) provided significantly greater reductions in total-C, LDL-C, Apo B, and non-HDL-C compared to rosuvastatin doses pooled (10-40 mg).] | LDL-C | Apo B | HDL-C | TG | Non-HDL-C
VYTORIN by dose
10/20 | 476 | -37 [p<0.05 vs. rosuvastatin 10 mg.] | -52 | -42 | +7 | -23 | -47
10/40 | 477 | -39 [p<0.05 vs. rosuvastatin 20 mg.] | -55 | -44 | +8 | -27 | -50
10/80 | 474 | -44 [p<0.05 vs. rosuvastatin 40 mg.] | -61 | -50 | +8 | -30 | -56
Rosuvastatin by dose
10 mg | 475 | -32 | -46 | -37 | +7 | -20 | -42
20 mg | 478 | -37 | -52 | -43 | +8 | -26 | -48
40 mg | 475 | -41 | -57 | -47 | +8 | -28 | -52

In a multicenter, double-blind, 24-week trial, 214 patients with type 2 diabetes mellitus treated with thiazolidinediones (rosiglitazone or pioglitazone) for a minimum of 3 months and simvastatin 20 mg for a minimum of 6 weeks were randomized to receive either simvastatin 40 mg or the coadministered active ingredients equivalent to VYTORIN 10/20. The median LDL-C and HbA1c levels at baseline were 89 mg/dL and 7.1%, respectively.

VYTORIN 10/20 was significantly more effective than doubling the dose of simvastatin to 40 mg. The median percent changes from baseline for VYTORIN vs. simvastatin were: LDL-C -25% and -5%; total-C -16% and -5%; Apo B -19% and -5%; and non-HDL-C -23% and -5%. Results for HDL-C and TG between the two treatment groups were not significantly different.

Ezetimibe

In two multicenter, double-blind, placebo-controlled, 12-week trials in 1719 patients with primary hyperlipidemia, ezetimibe significantly lowered total-C (-13%), LDL-C (-19%), Apo B (-14%), and TG (-8%), and increased HDL-C (+3%) compared to placebo. Reduction in LDL-C was consistent across age, sex, and baseline LDL-C.

Simvastatin

In two large, placebo-controlled clinical trials, the Scandinavian Simvastatin Survival Trial (N=4,444 patients) and the Heart Protection Trial (N=20,536 patients), the effects of treatment with simvastatin were assessed in patients at high risk of coronary events because of existing coronary heart disease, diabetes, peripheral vessel disease, history of stroke or other cerebrovascular disease. Simvastatin was proven to reduce: the risk of total mortality by reducing CHD deaths; the risk of non-fatal myocardial infarction and stroke; and the need for coronary and non-coronary revascularization procedures.

No incremental benefit of VYTORIN on cardiovascular morbidity and mortality over and above that demonstrated for simvastatin has been established.

Heterozygous Familial Hypercholesterolemia (HeFH) in Pediatric Patients

The effects of ezetimibe coadministered with simvastatin (n=126) compared to simvastatin monotherapy (n=122) have been evaluated in males and females with HeFH. In a multicenter, double-blind, controlled trial followed by an open-label phase, 142 males and 106 postmenarchal females, 10 to 17 years of age (mean age 14.2 years, 43% females, 82% White, 4% Asian, 2% Black or African American, 13% multi- racial; 14% identified as Hispanic or Latino ethnicity) with HeFH were randomized to receive either ezetimibe coadministered with simvastatin or simvastatin monotherapy. Inclusion in the trial required 1) a baseline LDL-C level between 160 and 400 mg/dL and 2) a medical history and clinical presentation consistent with HeFH. The mean baseline LDL-C value was 225 mg/dL (range: 161 to 351 mg/dL) in the ezetimibe coadministered with simvastatin group compared to 219 mg/dL (range: 149 to 336 mg/dL) in the simvastatin monotherapy group. The patients received coadministered ezetimibe and simvastatin (10 mg, 20 mg, or 40 mg) or simvastatin monotherapy (10 mg, 20 mg, or 40 mg) for 6 weeks, coadministered ezetimibe and 40- mg simvastatin or 40-mg simvastatin monotherapy for the next 27 weeks, and open-label coadministered ezetimibe and simvastatin (10 mg, 20 mg, or 40 mg) for 20 weeks thereafter.

The results of the trial at Week 6 are summarized in Table 13. Results at Week 33 were consistent with those at Week 6.

Table 13: Mean Percent Difference at Week 6 Between the Pooled ZETIA Coadministered with Simvastatin Group and the Pooled Simvastatin Monotherapy Group in Adolescent Patients with HeFH
 | Total-C | LDL-C | Apo B | Non-HDL-C
Mean percent difference between treatment groups | -12% | -15% | -12% | -14%
95% Confidence Interval | (-15%,-9%) | (-18%,-12%) | (-15%,-9%) | (-17%,-11%)

Homozygous Familial Hypercholesterolemia (HoFH) in Adults

A double-blind, randomized, 12-week trial was performed in patients with a clinical and/or genotypic diagnosis of HoFH. Data were analyzed from a subgroup of patients (n=14) receiving simvastatin 40 mg at baseline. Increasing the dose of simvastatin from 40 to 80 mg (n=5) produced a reduction of LDL-C of 13% from baseline on simvastatin 40 mg. Coadministered ezetimibe and simvastatin equivalent to VYTORIN (10/40 and 10/80 pooled, n=9), produced a reduction of LDL-C of 23% from baseline on simvastatin 40 mg. In those patients coadministered ezetimibe and simvastatin equivalent to VYTORIN (10/80, n=5), a reduction of LDL-C of 29% from baseline on simvastatin 40 mg was produced.

Chronic Kidney Disease (CKD) in Adults

The Trial of Heart and Renal Protection (SHARP) was a multinational, randomized, placebo-controlled, double-blind trial that investigated the effect of VYTORIN on the time to a first major vascular event (MVE) among 9438 patients with moderate to severe chronic kidney disease (approximately one-third on dialysis at baseline) who did not have a history of myocardial infarction or coronary revascularization. An MVE was defined as nonfatal MI, cardiac death, stroke, or any revascularization procedure. Patients were allocated to treatment using a method that took into account the distribution of 8 important baseline characteristics of patients already enrolled and minimized the imbalance of those characteristics across the groups.

For the first year, 9438 patients were allocated 4:4:1, to VYTORIN 10/20, placebo, or simvastatin 20 mg daily, respectively. The 1-year simvastatin arm enabled the comparison of VYTORIN to simvastatin with regard to safety and effect on lipid levels. At 1 year the simvastatin-only arm was re-allocated 1:1 to VYTORIN 10/20 or placebo. A total of 9270 patients were ever allocated to VYTORIN 10/20 (n=4650) or placebo (n=4620) during the trial. The median follow-up duration was 4.9 years. Patients had a mean age of 61 years; 63% were male, 72% were White, and 23% were diabetic; and, for those not on dialysis at baseline, the median serum creatinine was 2.5 mg/dL and the median estimated glomerular filtration rate (eGFR) was 25.6 mL/min/1.73 m^2, with 94% of patients having an eGFR < 45 mL/min/1.73m^2. Eligibility did not depend on lipid levels. Mean LDL-C at baseline was 108 mg/dL. At 1 year, the mean LDL-C was 26% lower in the simvastatin arm and 38% lower in the VYTORIN arm relative to placebo. At the midpoint of the trial (2.5 years), the mean LDL-C was 32% lower for VYTORIN relative to placebo. Patients no longer taking trial medication were included in all lipid measurements.

In the primary intent-to-treat analysis, 639 (15.2%) of 4193 patients initially allocated to VYTORIN and 749 (17.9%) of 4191 patients initially allocated to placebo experienced an MVE. This corresponded to a relative risk reduction of 16% (p=0.001) (see Figure 1). Similarly, 526 (11.3%) of 4650 patients ever allocated to VYTORIN and 619 (13.4%) of 4620 patients ever allocated to placebo experienced a major atherosclerotic event (MAE; a subset of the MVE composite that excluded non-coronary cardiac deaths and hemorrhagic stroke), corresponding to a relative risk reduction of 17% (p=0.002). The trial demonstrated that treatment with VYTORIN 10/20 mg versus placebo reduced the risk for MVE and MAE in this CKD population. The trial design precluded drawing conclusions regarding the independent contribution of either ezetimibe or simvastatin to the observed effect.

The treatment effect of VYTORIN on MVE was attenuated among patients on dialysis at baseline compared with those not on dialysis at baseline. Among 3023 patients on dialysis at baseline, VYTORIN reduced the risk of MVE by 6% (RR 0.94: 95% CI 0.80-1.09) compared with 22% (RR 0.78: 95% CI 0.69-0.89) among 6247 patients not on dialysis at baseline (interaction P=0.08).

Figure 1: Effect of VYTORIN on the Primary Endpoint of Risk of Major Vascular Events

The individual components of MVE in all patients ever allocated to VYTORIN or placebo are presented in Table 14.

Table 14: Number of First Events for Each Component of the Major Vascular Event Composite Endpoint in SHARP [Intention-to-treat analysis on all SHARP patients ever allocated to VYTORIN or placebo.]
Outcome | VYTORIN 10/20 (N=4650) | Placebo (N=4620) | Risk Ratio (95% CI) | P-value
Major Vascular Events | 701 (15.1%) | 814 (17.6%) | 0.85 (0.77-0.94) | 0.001
Nonfatal MI | 134 (2.9%) | 159 (3.4%) | 0.84 (0.66-1.05) | 0.12
Cardiac Death | 253 (5.4%) | 272 (5.9%) | 0.93 (0.78-1.10) | 0.38
Any Stroke | 171 (3.7%) | 210 (4.5%) | 0.81 (0.66-0.99) | 0.038
Non-hemorrhagic Stroke | 131 (2.8%) | 174 (3.8%) | 0.75 (0.60-0.94) | 0.011
Hemorrhagic Stroke | 45 (1.0%) | 37 (0.8%) | 1.21 (0.78-1.86) | 0.40
Any Revascularization | 284 (6.1%) | 352 (7.6%) | 0.79 (0.68-0.93) | 0.004

Among patients not on dialysis at baseline, VYTORIN did not reduce the risk of progressing to end-stage renal disease compared with placebo (RR 0.97: 95% CI 0.89-1.05).

Simvastatin Cardiovascular Outcome Trials in Adults at High Risk of Coronary Heart Disease Events

In a randomized, double-blind, placebo-controlled, multi-centered trial [the Scandinavian Simvastatin Survival Trial (Trial 4S)], the effect of therapy with simvastatin on total mortality was assessed in 4,444 adult patients with CHD (history of angina and/or a previous myocardial infarction) and baseline total cholesterol (total-C) between 212 and 309 mg/dL who were on a lipid-lowering diet. In Trial 4S, patients were treated with standard care, including lipid-lowering diet, and randomized to either simvastatin 20-40 mg/day (n=2,221) or placebo (n=2,223) for a median duration of 5.4 years.

- Simvastatin significantly reduced the risk of mortality by 30% (p=0.0003, 182 deaths in the simvastatin group vs 256 deaths in the placebo group). The risk of CHD mortality was significantly reduced by 42% (p=0.00001, 111 deaths in the simvastatin group vs 189 deaths in the placebo group). There was no statistically significant difference between groups in non-cardiovascular mortality.
- Simvastatin significantly reduced the risk for the secondary composite endpoint (time to first occurrence of CHD death, definite or probable hospital verified non-fatal MI, silent MI verified by ECG, or resuscitated cardiac arrest) by 34% (p<0.00001, 431 vs 622 patients with one or more events). Simvastatin reduced the risk of major coronary events to a similar extent across the range of baseline total and LDL cholesterol levels. The risk of having a hospital-verified non-fatal MI was reduced by 37%.
- Simvastatin significantly reduced the risk for undergoing myocardial revascularization procedures (coronary artery bypass grafting or percutaneous transluminal coronary angioplasty) by 37% (p<0.00001, 252 vs 383 patients).
- Simvastatin significantly reduced the risk of fatal plus non-fatal cerebrovascular events (combined stroke and transient ischemic attacks) by 28% (p=0.033, 75 vs 102 patients).
- Over the course of the trial, treatment with simvastatin led to mean reductions in total-C, LDL-C and triglycerides (TG) of 25%, 35%, and 10%, respectively, and a mean increase in high-density lipoprotein cholesterol (HDL-C) of 8%. In contrast, treatment with placebo led to increases in total- C, LDL-C and TG of 1%, 1%, and 7%, respectively.
- Because there were only 53 female deaths (approximately 18% of the trial population was female), the effect of simvastatin on mortality in females could not be adequately assessed. However, simvastatin significantly reduced the risk of having major coronary events in females by 34% (60 vs 91 women with one or more event).
- Simvastatin resulted in similar decreases in relative risk for total mortality, CHD mortality, and major coronary events in geriatric patients (≥65 years) compared with younger adults.

The Heart Protection Trial (Trial HPS) was a randomized, placebo-controlled, double-blind, multi- centered trial with a mean duration of 5 years conducted in 10,269 patients on simvastatin 40 mg and 10,267 on placebo. Patients had a mean age of 64 years (range 40-80 years old), 97% were White, and were at high risk of developing a major coronary event because of existing CHD (65%), diabetes (Type 2, 26%; Type 1, 3%), history of stroke or other cerebrovascular disease (16%), peripheral vascular disease (33%), or they were males ≥65 years with hypertension in (6%). At baseline:

- 3,421 patients (17%) had LDL-C levels below 100 mg/dL, including 953 (5%) below 80 mg/dL; and
- 10,047 patients (49%) had levels greater than 130 mg/dL.

Patients were randomized to simvastatin or placebo using a covariate adaptive method which considered the distribution of 10 important baseline characteristics of patients already enrolled.

The Trial HPS results showed that simvastatin 40 mg/day significantly reduced: total and CHD mortality; and non-fatal MI, stroke, and revascularization procedures (coronary and non-coronary) (see Table 15).

Table 15: CHD Mortality and Cardiovascular Events in Adult Patients with High Risk of Developing a Major Coronary Event in Trial HPS
Endpoint | Simvastatin (N=10,269) n (%) [n = number of patients with indicated event] | Placebo (N=10,267) n (%) | Risk Reduction (%) (95% CI) | p-Value
Primary
Mortality | 1,328 (12.9%) | 1,507 (14.7%) | 13% (6-19%) | p=0.0003
CHD mortality | 587 (5.7%) | 707 (6.9%) | 18% (8-26%) | p=0.0005
Secondary
Non-fatal MI | 357 (3.5%) | 574 (5.6%) | 38% (30-46%) | p<0.0001
Stroke | 444 (4.3%) | 585 (5.7%) | 25% (15-34%) | p<0.0001
Tertiary
Coronary revascularization | 513 (5%) | 725 (7.1%) | 30% (22-38%) | p<0.0001
Peripheral and other non-coronary revascularization | 450 (4.4%) | 532 (5.2%) | 16% (5-26%) | p=0.006

Two composite endpoints were defined to have enough events to assess relative risk reductions across a range of baseline characteristics:

- Major coronary events (MCE) was comprised of CHD mortality and non-fatal MI. Analyzed by time-to-first event; 898 patients (8.7%) treated with simvastatin had events and 1,212 patients (11.8%) treated with placebo had events.
- Major vascular events (MVE) was comprised of MCE, stroke, and revascularization procedures including coronary, peripheral and other non-coronary procedures. Analyzed by time-to-first event; 2,033 patients (19.8%) treated with simvastatin had events and 2,585 patients (25.2%) on placebo had events.

Simvastatin use led to significant relative risk reductions for both composite endpoints (27% for MCE and 24% for MVE, p<0.0001) and for all components of the composite endpoints. The risk reductions produced by simvastatin in both MCE and MVE were evident and consistent regardless of cardiovascular disease related medical history at trial entry (i.e., CHD alone; or peripheral vascular disease, cerebrovascular disease, diabetes or treated hypertension, with or without CHD), gender, age, baseline levels of LDL-C, baseline concomitant cardiovascular medications (i.e., aspirin, beta blockers, or calcium channel blockers), smoking status, or obesity. Patients with diabetes showed risk reductions for MCE and MVE due to simvastatin treatment regardless of baseline HbA1c levels or obesity.

16 HOW SUPPLIED/STORAGE AND HANDLING

VYTORIN tablets are supplied as follows:

Strength | How Supplied | NDC | Tablet Description
10/10 mg | unit of use bottles of 30 | 78206-174-01 | white to off-white capsule-shaped tablets with code “311” on one side
10/10 mg | unit of use bottles of 90 | 78206-174-02 | white to off-white capsule-shaped tablets with code “311” on one side
10/20 mg | unit of use bottles of 30 | 78206-175-01 | white to off-white capsule-shaped tablets with code “312” on one side
10/20 mg | unit of use bottles of 90 | 78206-175-02 | white to off-white capsule-shaped tablets with code “312” on one side
10/40 mg | unit of use bottles of 30 | 78206-176-01 | white to off-white capsule-shaped tablets with code “313” on one side
10/40 mg | unit of use bottles of 90 | 78206-176-02 | white to off-white capsule-shaped tablets with code “313” on one side
10/80 mg | unit of use bottles of 30 | 78206-177-01 | white to off-white capsule-shaped tablets with code “315” on one side
10/80 mg | unit of use bottles of 90 | 78206-177-02 | white to off-white capsule-shaped tablets with code “315” on one side

Storage

Store at 68°F to 77°F (20°C to 25°C). [See USP Controlled Room Temperature.] Keep container tightly closed.

17 PATIENT COUNSELING INFORMATION

Advise the patient to read the FDA-approved patient labeling (Patient Information).

Myopathy and Rhabdomyolysis

Advise patients that VYTORIN may cause myopathy and rhabdomyolysis. Inform patients taking the 80 mg daily dose of simvastatin that they are at an increased risk. Inform patients that the risk is also increased when taking certain types of medication or consuming grapefruit juice and they should discuss all medication, both prescription and over the counter, with their healthcare provider. Instruct patients to inform other healthcare providers prescribing a new medication or increasing the dose of an existing medication that they are taking VYTORIN. Instruct patients to promptly report any unexplained muscle pain, tenderness or weakness particularly if accompanied by malaise or fever [see Contraindications (4), Warnings and Precautions (5.1), and Drug Interactions (7.1)].

Hepatic Dysfunction

Inform patients that VYTORIN may cause liver enzyme elevations and possibly liver failure. Advise patients to promptly report fatigue, anorexia, right upper abdominal discomfort, dark urine or jaundice [see Warnings and Precautions (5.3)].

Increases in HbA1c and Fasting Serum Glucose Levels

Inform patients that increases in HbA1c and fasting serum glucose levels may occur with VYTORIN. Encourage patients to optimize lifestyle measures, including regular exercise, maintaining a healthy body weight, and making healthy food choices [see Warnings and Precautions (5.4)].

Pregnancy

Advise pregnant patients and patients who can become pregnant of the potential risk to a fetus. Advise patients to inform their healthcare provider of a known or suspected pregnancy to discuss if VYTORIN should be discontinued [see Use in Specific Populations (8.1)].

Lactation

Advise patients that breastfeeding is not recommended during treatment with VYTORIN [see Use in Specific Populations (8.2)].

Missed Dose

Instruct patients to take VYTORIN only as prescribed. If a dose is missed, it should be taken as soon as possible. Advise patients not to double their next dose.

Distributed by: Organon LLC, a subsidiary of
ORGANON & Co.,
Jersey City, NJ 07302, USA

For patent information: www.organon.com/our-solutions/patent/

© 2024 Organon group of companies. All rights reserved.

uspi-og0653a-t-2403r002

PATIENT INFORMATION
VYTORIN® [VI-tor-in]
(ezetimibe and simvastatin)
tablets, for oral use

Read this Information carefully before you start taking VYTORIN® and each time you get a VYTORIN. There may be new information. This information does not take the place of talking with your healthcare provider about your medical condition or your treatment. If you have any questions about VYTORIN, ask your healthcare provider. Only your healthcare provider can determine if VYTORIN is right for you.

What is VYTORIN?

VYTORIN is a prescription medicine that contains the cholesterol lowering medicines, simvastatin and ezetimibe:

- VYTORIN is used along with diet to lower elevated low-density lipoprotein cholesterol (LDL-C) or bad cholesterol in:
  - adults with primary hyperlipidemia (high level of fats in your blood).
  - adults and children 10 years of age and older with heterozygous familial hypercholesterolemia (HeFH). HeFH is an inherited condition that causes high levels of bad cholesterol.
- VYTORIN is also used with other cholesterol lowering treatments to lower elevated LDL-C levels in adults with homozygous familial hypercholesterolemia (HoFH). HoFH is an inherited condition that causes high levels of bad cholesterol.
- Simvastatin when used as a component of VYTORIN is used to lower:
  - the risk of death by lowering the risk of heart disease death.
  - the risk of heart attacks and strokes.
  - the need for certain types of heart and blood vessel procedures to improve blood flow called arterial revascularization in people with known heart, cerebrovascular disease (conditions that affect blood flow and the blood vessels in the brain), peripheral vascular disease (a blood circulation disorder that causes the blood vessels outside of your heart and brain to narrow, block, or spasm), and diabetes, who are at high risk for heart disease problems.

The safety and effectiveness of VYTORIN has not been established in children younger than 10 years of age with inherited heterozygous familial hypercholesterolemia (HeFH) or other types of hyperlipidemia.

Do not take VYTORIN if you:

- take certain medicines called CYP3A4 inhibitors such as:
  - certain antifungal medicines (such as itraconazole, ketoconazole, posaconazole, voriconazole).
  - certain antibiotics (including erythromycin, clarithromycin, telithromycin).
  - HIV protease inhibitors (such as indinavir, nelfinavir, ritonavir, saquinavir, tipranavir, or atazanavir and cobicistat-containing products such as (elvitegravir/cobicistat/emtricitabine/tenofovir disoproxil fumarate).
  - certain hepatitis C virus protease inhibitors (such as boceprevir or telaprevir).
  - the antidepressant nefazodone.
- take medicines called cyclosporine, danazol, or gemfibrozil.
- have liver problems.
- are allergic to simvastatin, ezetimibe, or any of the ingredients in VYTORIN. See the end of this Patient Information leaflet for a complete list of ingredients in VYTORIN.

Ask your healthcare provider or pharmacist if you are not sure if your medicine is listed above.

Before you take VYTORIN, tell your healthcare provider about all of your medical conditions, including if you:

- have unexplained muscle aches or weakness.
- have or have had myasthenia gravis (a disease causing general muscle weakness including in some cases muscles used for breathing), ocular myasthenia (a disease causing eye muscle weakness).
- have kidney problems.
- have liver problems or drink more than 2 glasses of alcohol daily.
- have thyroid problems.
- are 65 years of age or older.
- are of Chinese descent.
- are pregnant or plan to become pregnant. If you become pregnant while taking VYTORIN, call your healthcare provider right away to discuss stopping VYTORIN.
- are breastfeeding or plan to breastfeed. It is not known if VYTORIN passes into your breast milk. Do not breastfeed while taking VYTORIN.

Tell your healthcare provider about all the medicines you take, including prescription and over-the-counter medicines, vitamins, and herbal supplements. Talk to your healthcare provider before you start taking any new medicines.

Tell your healthcare provider who prescribes VYTORIN if another healthcare provider increases the dose of another medicine you are taking.

VYTORIN may affect the way other medicines work, and other medicines may affect how VYTORIN works. Especially tell your healthcare provider if you take:

- digoxin (a drug used to treat irregular heartbeat).
- coumarin anticoagulants (drugs that prevent blood clots, such as warfarin).
- fibric acid derivatives (such as fenofibrate).

Taking VYTORIN with certain substances can also increase the risk of muscle problems. Especially tell your healthcare provider if you take:

- amiodarone or dronedarone (medicines used to treat an irregular heartbeat).
- verapamil, diltiazem, amlodipine, or ranolazine (medicines used to treat high blood pressure, chest pain associated with heart disease, or other heart conditions).
- lomitapide (a medicine used to treat a serious and rare genetic cholesterol condition).
- daptomycin (a drug used to treat complicated skin and bloodstream infections).
- large doses of niacin or nicotinic acid, especially if you are of Chinese descent.
- colchicine (a medicine used to treat gout).
- grapefruit juice.

Ask your healthcare provider or pharmacist for a list of medicines if you are not sure. Know the medicines you take. Keep a list of them to show your healthcare provider and pharmacist when you get a new medicine.

How should I take VYTORIN?

- Take VYTORIN exactly as your healthcare provider tells you to take it.
- Do not change your dose or stop taking VYTORIN without talking to your healthcare provider.
- Take VYTORIN 1 time each day in the evening.
- If you miss a dose, take it as soon as you remember. If you do not remember until it is time for your next dose, skip the missed dose and go back to your regular schedule. Do not take 2 doses of VYTORIN at the same time. Talk with your healthcare provider if you have questions about a missed dose.
- While taking VYTORIN, continue to follow your cholesterol-lowering diet and to exercise as your healthcare provider told you to.
- Your healthcare provider may do blood tests to check your cholesterol while you take VYTORIN. Your healthcare provider may change your dose of VYTORIN if needed.

If you take too much VYTORIN, call your healthcare provider or Poison Help Line at 1-800-222-1222 or go to the nearest hospital emergency room right away.

What are the possible side effects of VYTORIN?

VYTORIN may cause serious side effects including:

- Muscle pain, tenderness, and weakness (myopathy). Muscle problems, including muscle breakdown, can be serious in some people and rarely cause kidney damage that can lead to death.
  Tell your healthcare provider right away if:
  - you have unexplained muscle pain, tenderness, or weakness, especially if you have a fever or feel more tired than usual, while you take VYTORIN.
  - you have muscle problems that do not go away even after your healthcare provider has advised you to stop taking VYTORIN. Your healthcare provider may do further tests to diagnose the cause of your muscle problems.
    Your chances of getting muscle problems are higher if you:
  - are taking certain other medicines while you take VYTORIN.
  - are 65 years of age or older.
  - are female.
  - have thyroid problems (hypothyroidism) that are not controlled.
  - have kidney problems.
  - are taking higher doses of VYTORIN.
  - are Chinese.
- Liver problems. Your healthcare provider should do blood tests to check your liver before you start taking VYTORIN and if you have any symptoms of liver problems while you take VYTORIN. Call your healthcare provider right away if you have the following symptoms of liver problems:
  - feeling tired or weak
  - loss of appetite
  - right-sided upper belly pain
  - dark urine
  - yellowing of your skin or the whites of your eyes
- increase in blood sugar (glucose) levels). VYTORIN may cause an increase in your blood sugar levels.

The most common side effects of VYTORIN include:

- headache
- increased liver enzyme levels
- muscle pain
- upper respiratory infection
- diarrhea

Tell your healthcare provider if you have any side effect that bothers you or does not go away.

These are not all the possible side effects of VYTORIN.

Call your doctor for medical advice about side effects. You may report side effects to FDA at 1-800-FDA-1088.

How should I store VYTORIN?

- Store VYTORIN at room temperature between 68ºF to 77ºF (20ºC to 25ºC).
- Keep VYTORIN in its original container until you use it.
- Keep VYTORIN in a tightly closed container.

Keep VYTORIN and all medicines out of the reach of children.

General information about safe and effective use of VYTORIN.

Medicines are sometimes prescribed for purposes other than those listed in a Patient Information leaflet. Do not use VYTORIN for a condition for which it was not prescribed. Do not give VYTORIN to other people, even if they have the same symptoms that you have. It may harm them.

You can ask your pharmacist or healthcare provider for information about VYTORIN that is written for health professionals.

What are the ingredients in VYTORIN?

Active Ingredients: ezetimibe and simvastatin.

Inactive Ingredients: butylated hydroxyanisole, citric acid monohydrate, croscarmellose sodium, hypromellose, lactose monohydrate, magnesium stearate, microcrystalline cellulose, and propyl gallate.

Distributed by: Organon LLC, a subsidiary of
ORGANON & Co.,
Jersey City, NJ 07302, USA

For patent information: www.organon.com/our-solutions/patent/

© 2024 Organon group of companies. All rights reserved.

For more information, go to www.organon.com/our-focus/products-list/ or call 1-844-674-3200.

usppi-og0653a-t-2402r001

This Patient Information has been approved by the U.S. Food and Drug Administration.

Revised: 2/2024

PRINCIPAL DISPLAY PANEL - 10 mg /10 mg Tablet Bottle Label

NDC 78206-174-01

Vytorin®
(ezetimibe and
simvastatin) tablets

10 mg /10 mg

Each tablet contains 10 mg ezetimibe and
10 mg simvastatin.

Rx only

30 Tablets

PRINCIPAL DISPLAY PANEL - 10 mg /20 mg Tablet Bottle Label

NDC 78206-175-01

Vytorin®
(ezetimibe and
simvastatin) tablets

10 mg /20 mg

Each tablet contains 10 mg ezetimibe and
20 mg simvastatin.

Rx only

30 Tablets

PRINCIPAL DISPLAY PANEL - 10 mg /40 mg Tablet Bottle Label

NDC 78206-176-01

Vytorin®
(ezetimibe and
simvastatin) tablets

10 mg /40 mg

Each tablet contains 10 mg ezetimibe and
40 mg simvastatin.

Rx only

30 Tablets

PRINCIPAL DISPLAY PANEL - 10 mg /80 mg Tablet Bottle Label

NDC 78206-177-01

Vytorin®
(ezetimibe and
simvastatin) tablets

10 mg /80 mg

Each tablet contains 10 mg ezetimibe and
80 mg simvastatin.

Rx only

30 Tablets